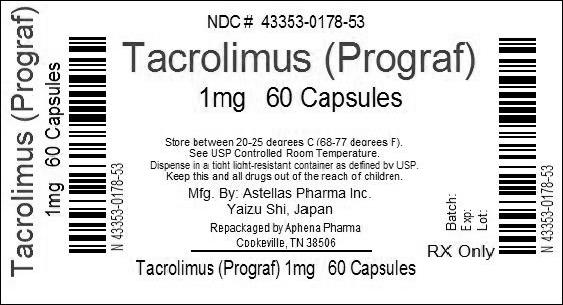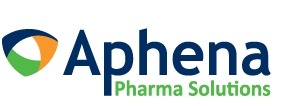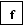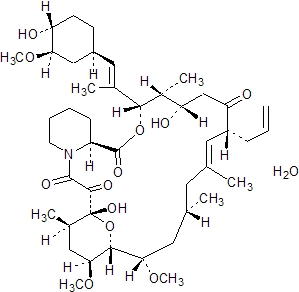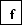 DRUG LABEL: Prograf
NDC: 43353-178 | Form: CAPSULE, GELATIN COATED
Manufacturer: Aphena Pharma Solutions - Tennessee, LLC
Category: prescription | Type: HUMAN PRESCRIPTION DRUG LABEL
Date: 20140520

ACTIVE INGREDIENTS: TACROLIMUS 1 mg/1 1

HIGHLIGHTS OF PRESCRIBING INFORMATION

These highlights do not include all the information needed to use PROGRAF safely and effectively. See full prescribing information for PROGRAF.
PROGRAF® (tacrolimus) capsules, USP
PROGRAF® (tacrolimus) injection, (for intravenous use)
Initial U.S. Approval: 1994

RECENT MAJOR CHANGES

Warnings and Precautions, Use with CYP3A4 Inhibitors and Inducers (5.13) 08/2013
Warnings and Precautions, QT Prolongation (5.14) 08/2013
Warnings and Precautions, Gastrointestinal Perforation (5.18) 08/2013

BOXED WARNING - MALIGNANCIES AND SERIOUS INFECTIONS

WARNING: MALIGNANCIES AND SERIOUS INFECTIONS

See full prescribing information for complete boxed warning

- Increased risk of development of lymphoma and other malignancies, particularly of the skin, due to immunosuppression (5.2)
- Increased susceptibility to bacterial, viral, fungal, and protozoal infections, including opportunistic infections (5.3, 5.4, 5.5)
- Only physicians experienced in immunosuppressive therapy and management of organ transplant patients should prescribe Prograf (5.1)

1 INDICATIONS AND USAGE

Prograf is a calcineurin-inhibitor immunosuppressant indicated for

- Prophylaxis of organ rejection in patients receiving allogeneic liver, kidney or heart transplants (1.1, 1.2, 1.3)
- Use concomitantly with adrenal corticosteroids; in kidney and heart transplant, use in conjunction with azathioprine or mycophenolate mofetil (MMF) (1.1, 1.2, 1.3)
- Limitations of Use (1.4):
  ∘ Do not use simultaneously with cyclosporine
  ∘ Intravenous use reserved for patients who can not tolerate capsules orally
  ∘ Use with sirolimus is not recommended in liver and heart transplant; use with sirolimus in kidney transplant has not been established

2 DOSAGE AND ADMINISTRATION

Summary of Initial Oral Dosage Recommendation and Observed Whole Blood Trough Concentrations (2.1, 2.2).

Patient Population | Recommended Initial; Oral Dosage (two divided doses every 12 hours) | Observed Whole Blood Trough Concentrations
Adult Kidney transplant
In combination with azathioprine | 0.2 mg/kg/day | month 1-3: 7-20 ng/mL; month 4-12: 5-15 ng/mL
In combination with MMF/IL-2 receptor antagonist | 0.1 mg/kg/day | month 1-12: 4-11 ng/mL
Adult Liver transplant | 0.10-0.15 mg/kg/day | month 1-12: 5-20 ng/mL
Pediatric Liver transplant | 0.15-0.20 mg/kg/day | month 1-12: 5-20 ng/mL
Adult Heart transplant | 0.075 mg/kg/day | month 1-3: 10-20 ng/mL; month ≥4: 5-15 ng/mL

- Careful and frequent monitoring of tacrolimus trough concentrations is recommended; Black patients may require higher doses in order to achieve comparable trough concentrations (2.1)
- Hepatic/Renal impaired patients should receive doses at the lowest value of the recommended initial oral dosing range (2.3, 2.4)
- Administer capsules consistently with or without food; do not drink grapefruit juice (2.5, 7.2)

3 DOSAGE FORMS AND STRENGTHS

- Capsules: 0.5 mg, 1 mg and 5 mg (3)
- Injection: 5 mg/mL (3)

4 CONTRAINDICATIONS

- Hypersensitivity to tacrolimus or HCO-60 (polyoxyl 60 hydrogenated castor oil) (4)

5 WARNINGS AND PRECAUTIONS

- Lymphoma and Other Malignancies: Risk of lymphomas, including post transplant lymphoproliferative disorder (PLTD); appears related to intensity and duration of use. Avoid prolonged exposure to UV light and sunlight (5.2)
- Serious infections: Increased risk of bacterial, viral, fungal and protozoal infections, including opportunistic infections: combination immunosuppression should be used with caution (5.3)
- Polyoma Virus Infections: Serious, sometimes fatal outcomes, including polyoma virus-associated nephropathy (PVAN), mostly due to BK virus, and JC virus-associated progressive multifocal leukoencephalopathy (PML); consider reducing immunosuppression (5.4)
- Cytomegalovirus (CMV) Infections: Increased risk of CMV viremia and disease; consider reducing immunosuppression (5.5)
- New Onset Diabetes After Transplant: Monitor blood glucose (5.6)
- Nephrotoxicity: Acute and/or chronic; reduce the dose; use caution with other nephrotoxic drugs (5.7)
- Neurotoxicity: Risk of Posterior Reversible Encephalopathy Syndrome, monitor for neurologic abnormalities; reduce or discontinue Prograf and other immunosuppressants (5.8)
- Hyperkalemia: Monitor serum potassium levels. Careful consideration should be given prior to use of other agents also associated with hyperkalemia (5.9)
- Hypertension: May require antihypertensive therapy. Monitor relevant drug-drug interactions (5.10)
- Anaphylactic Reactions with IV formulation: Observe patients receiving Prograf injection for signs and symptoms of anaphylaxis (5.11)
- Use with Sirolimus: Not recommended in liver and heart transplant due to increased risk of serious adverse reactions (5.12)
- Myocardial Hypertrophy: Consider dosage reduction or discontinuation (5.15)
- Immunizations: Use of live vaccines should be avoided (5.16)
- Pure Red Cell Aplasia: Discontinuation should be considered (5.17)

6 ADVERSE REACTIONS

- Kidney Transplant: The most common adverse reactions (≥ 30%) were infection, tremor, hypertension, abnormal renal function, constipation, diarrhea, headache, abdominal pain, insomnia, nausea, hypomagnesemia, urinary tract infection, hypophosphatemia, peripheral edema, asthenia, pain, hyperlipidemia, hyperkalemia, anemia (6.1)
- Liver Transplant: The most common adverse reactions (≥ 40%) were tremor, headache, diarrhea, hypertension, nausea, abnormal renal function, abdominal pain, insomnia, paresthesia, anemia, pain, fever, asthenia, hyperkalemia, hypomagnesemia, and hyperglycemia (6.1)
- Heart Transplant: The most common adverse reactions (≥ 15%) were abnormal renal function, hypertension, diabetes mellitus, CMV infection, tremor, hyperglycemia, leukopenia, infection, anemia, bronchitis, pericardial effusion, urinary tract infection and hyperlipemia (6.1)

To report SUSPECTED ADVERSE REACTIONS, contact Astellas Pharma US, Inc at 1-800-727-7003 or FDA at 1-800-FDA-1088 or www.fda.gov/medwatch.

7 DRUG INTERACTIONS

- Mycophenolic Acid Products: Can increase MPA exposure after crossover from cyclosporine to Prograf; monitor for MPA-related adverse reactions and adjust MMF or MPA-dose as needed (7.1)
- Nelfinavir and Grapefruit Juice: Increased tacrolimus concentrations via CYP3A inhibition; avoid concomitant use (7.2, 7.3)
- CYP3A Inhibitors: Increased tacrolimus concentrations; monitor concentrations and adjust tacrolimus dose as needed with concomitant use (5.13, 7.3, 7.4, 7.5, 7.6)
- CYP3A4 Inducers: Decreased tacrolimus concentrations; monitor concentrations and adjust tacrolimus dose as needed with concomitant use (5.13, 7.7, 7.8, 7.9)

8 USE IN SPECIFIC POPULATIONS

- Pregnancy: Based on animal data may cause fetal harm. Use only if the potential benefit justifies the risk (8.1)
- Nursing Mothers: Discontinue nursing taking into consideration importance of drug to mother (8.3)
- Hepatic/Renal impaired patients: Administer at the lower end of the recommended starting dose. Monitor renal function in patients with impaired renal function (2.3, 2.4, 8.6, 8.7)

FULL PRESCRIBING INFORMATION

BOXED WARNING - MALIGNANCIES AND SERIOUS INFECTIONS

- Increased risk of development of lymphoma and other malignancies, particularly of the skin, due to immunosuppression [see Warnings and Precautions (5.2)].
- Increased susceptibility to bacterial, viral, fungal, and protozoal infections, including opportunistic infections [see Warnings and Precautions (5.3, 5.4, 5.5)].
- Only physicians experienced in immunosuppressive therapy and management of organ transplant patients should prescribe Prograf. Patients receiving the drug should be managed in facilities equipped and staffed with adequate laboratory and supportive medical resources. The physician responsible for maintenance therapy should have complete information requisite for the follow-up of the patient [see Warnings and Precautions (5.1)].

1 INDICATIONS AND USAGE

1.1 Prophylaxis of Organ Rejection in Kidney Transplant

Prograf is indicated for the prophylaxis of organ rejection in patients receiving allogeneic kidney transplants. It is recommended that Prograf be used concomitantly with azathioprine or mycophenolate mofetil (MMF) and adrenal corticosteroids [see Clinical Studies (14.1)]. Therapeutic drug monitoring is recommended for all patients receiving Prograf [see Dosage and Administration (2.6)].

1.2 Prophylaxis of Organ Rejection in Liver Transplant

Prograf is indicated for the prophylaxis of organ rejection in patients receiving allogeneic liver transplants. It is recommended that Prograf be used concomitantly with adrenal corticosteroids [see Clinical Studies (14.2)]. Therapeutic drug monitoring is recommended for all patients receiving Prograf [see Dosage and Administration (2.6)].

1.3 Prophylaxis of Organ Rejection in Heart Transplant

Prograf is indicated for the prophylaxis of organ rejection in patients receiving allogeneic heart transplants. It is recommended that Prograf be used concomitantly with azathioprine or mycophenolate mofetil (MMF) and adrenal corticosteroids [see Clinical Studies (14.3)]. Therapeutic drug monitoring is recommended for all patients receiving Prograf [see Dosage and Administration (2.6)].

1.4 Limitations of Use

Prograf should not be used simultaneously with cyclosporine [see Dosage and Administration (2.5)].

Prograf injection should be reserved for patients unable to take Prograf capsules orally [see Dosage and Administration (2.1) and Warnings and Precautions (5.11)].

Use with sirolimus is not recommended in liver and heart transplant. The safety and efficacy of Prograf with sirolimus has not been established in kidney transplant [see Warnings and Precautions (5.12)].

2 DOSAGE AND ADMINISTRATION

2.1 Dosage in Adult Kidney, Liver, or Heart Transplant Patients

The initial oral dosage recommendations for adult patients with kidney, liver, or heart transplants along with recommendations for whole blood trough concentrations are shown in Table 1. The initial dose of Prograf should be administered no sooner than 6 hours after transplantation in the liver and heart transplant patients. In kidney transplant patients, the initial dose of Prograf may be administered within 24 hours of transplantation, but should be delayed until renal function has recovered. For blood concentration monitoring details see Dosage and Administration (2.6).

Table 1. Summary of Initial Oral Dosage Recommendations and Observed Whole Blood Trough Concentrations in Adults
Patient Population | Recommended Prograf Initial; Oral Dosage; Note: daily doses should be administered as two divided doses, every 12 hours | Observed Tacrolimus Whole Blood Trough Concentrations
Adult kidney transplant patients
In combination with azathioprine | 0.2 mg/kg/day | month 1-3: 7-20 ng/mL; month 4-12: 5-15 ng/mL
In combination with MMF/IL-2 receptor antagonist [In a second smaller trial, the initial dose of tacrolimus was 0.15-0.2 mg/kg/day and observed tacrolimus concentrations were 6-16 ng/mL during month 1-3 and 5-12 ng/mL during month 4-12 [see Clinical Studies (14.1)].] | 0.1 mg/kg/day | month 1-12: 4-11 ng/mL
Adult liver transplant patients | 0.10-0.15 mg/kg/day | month 1-12: 5-20 ng/mL
Adult heart transplant patients | 0.075 mg/kg/day | month 1-3: 10-20 ng/mL; month ≥4: 5-15 ng/mL

Dosing should be titrated based on clinical assessments of rejection and tolerability. Lower Prograf dosages than the recommended initial dosage may be sufficient as maintenance therapy. Adjunct therapy with adrenal corticosteroids is recommended early post-transplant.

The data in kidney transplant patients indicate that the Black patients required a higher dose to attain comparable trough concentrations compared to Caucasian patients (Table 2).

Table 2. Comparative Dose and Trough Concentrations Based on Race
Time After Transplant | Caucasian; n=114 |  | Black; n=56
Time After Transplant | Dose; (mg/kg) | Trough Concentrations; (ng/mL) | Dose; (mg/kg) | Trough Concentrations (ng/mL)
Day 7 | 0.18 | 12.0 | 0.23 | 10.9
Month 1 | 0.17 | 12.8 | 0.26 | 12.9
Month 6 | 0.14 | 11.8 | 0.24 | 11.5
Month 12 | 0.13 | 10.1 | 0.19 | 11.0

Initial Dose – Injection

Prograf injection should be used only as a continuous IV infusion and when the patient cannot tolerate oral administration of Prograf capsules. Prograf injection should be discontinued as soon as the patient can tolerate oral administration of Prograf capsules, usually within 2-3 days. In a patient receiving an IV infusion, the first dose of oral therapy should be given 8-12 hours after discontinuing the IV infusion.

The observed trough concentrations described above pertain to oral administration of Prograf only; while monitoring Prograf concentrations in patients receiving Prograf injection as a continuous IV infusion may have some utility, the observed concentrations will not represent comparable exposures to those estimated by the trough concentrations observed in patients on oral therapy.

The recommended starting dose of Prograf injection is 0.03-0.05 mg/kg/day in kidney and liver transplant and 0.01 mg/kg/day in heart transplant given as a continuous IV infusion. Adult patients should receive doses at the lower end of the dosing range. Concomitant adrenal corticosteroid therapy is recommended early post-transplantation.

Anaphylactic reactions have occurred with injectables containing castor oil derivatives, such as Prograf injection [see Warnings and Precautions (5.11)].

2.2 Dosage in Pediatric Liver Transplant Patients

The initial oral dosage recommendations for pediatric patients with liver transplants along with recommendations for whole blood trough concentrations are shown in Table 3. For blood concentration monitoring details see Dosage and Administration (2.6). If necessary, pediatric patients may start on an IV dose of 0.03-0.05 mg/kg/day.

Table 3. Summary of Initial Oral Dosage Recommendations and Observed Whole Blood Trough Concentrations in Children
Patient Population | Recommended Prograf Initial Oral Dosage; Note: daily doses should be administered as two divided doses, every 12 hours | Observed Tacrolimus Whole Blood Trough Concentrations
Pediatric liver transplant patients | 0.15-0.20 mg/kg/day | Month 1-12: 5-20 ng/mL

Pediatric liver transplantation patients without pre-existing renal or hepatic dysfunction have required and tolerated higher doses than adults to achieve similar blood concentrations.

Experience in pediatric kidney and heart transplantation patients is limited.

2.3 Dosage Adjustment in Patients with Renal Impairment

Due to its potential for nephrotoxicity, consideration should be given to dosing Prograf at the lower end of the therapeutic dosing range in patients who have received a liver or heart transplant and have pre-existing renal impairment. Further reductions in dose below the targeted range may be required.

In kidney transplant patients with post-operative oliguria, the initial dose of Prograf should be administered no sooner than 6 hours and within 24 hours of transplantation, but may be delayed until renal function shows evidence of recovery.

2.4 Dosage Adjustments in Patients with Hepatic Impairment

Due to the reduced clearance and prolonged half-life, patients with severe hepatic impairment (Child Pugh ≥ 10) may require lower doses of Prograf. Close monitoring of blood concentrations is warranted.

The use of Prograf in liver transplant recipients experiencing post-transplant hepatic impairment may be associated with increased risk of developing renal insufficiency related to high whole-blood concentrations of tacrolimus. These patients should be monitored closely and dosage adjustments should be considered. Some evidence suggests that lower doses should be used in these patients [see Dosage and Administration (2.1), Use in Specific Populations (8.7) and Clinical Pharmacology (12.3)].

2.5 Administration Instructions

It is recommended that patients initiate oral therapy with Prograf capsules if possible.

Initial dosage and observed tacrolimus whole blood trough concentrations for adults are shown in Table 1 and for pediatrics in Table 3 [see Dosage and Administration (2.1, 2.2)]; for blood concentration monitoring details in kidney transplant patients [see Dosage and Administration (2.1)].

It is important to take Prograf capsules consistently every day either with or without food because the presence and composition of food decreases the bioavailability of Prograf [see Clinical Pharmacology (12.3)].

Patients should not eat grapefruit or drink grapefruit juice in combination with Prograf [see Drug Interactions (7.2)].

Prograf should not be used simultaneously with cyclosporine. Prograf or cyclosporine should be discontinued at least 24 hours before initiating the other. In the presence of elevated Prograf or cyclosporine concentrations, dosing with the other drug usually should be further delayed.

In patients unable to take oral Prograf capsules, therapy may be initiated with Prograf injection as a continuous IV infusion. If IV therapy is necessary, conversion from IV to oral Prograf is recommended as soon as oral therapy can be tolerated. This usually occurs within 2-3 days. In patients receiving an IV infusion, the first dose of oral therapy should be given 8-12 hours after discontinuing the IV infusion.

2.6 Therapeutic Drug Monitoring

Monitoring of tacrolimus blood concentrations in conjunction with other laboratory and clinical parameters is considered an essential aid to patient management for the evaluation of rejection, toxicity, dose adjustments and compliance. Observed whole blood trough concentrations can be found in Table 1. Factors influencing frequency of monitoring include but are not limited to hepatic or renal dysfunction, the addition or discontinuation of potentially interacting drugs and the post-transplant time. Blood concentration monitoring is not a replacement for renal and liver function monitoring and tissue biopsies. Data from clinical trials show that tacrolimus whole blood concentrations were most variable during the first week post-transplantation.

The relative risks of toxicity and efficacy failure are related to tacrolimus whole blood trough concentrations. Therefore, monitoring of whole blood trough concentrations is recommended to assist in the clinical evaluation of toxicity and efficacy failure.

Methods commonly used for the assay of tacrolimus include high performance liquid chromatography with tandem mass spectrometric detection (HPLC/MS/MS) and immunoassays. Immunoassays may react with metabolites as well as parent compound. Therefore assay results obtained with immunoassays may have a positive bias relative to results of HPLC/MS. The bias may depend upon the specific assay and laboratory. Comparison of the concentrations in published literature to patient concentrations using the current assays must be made with detailed knowledge of the assay methods and biological matrices employed. Whole blood is the matrix of choice and specimens should be collected into tubes containing ethylene diamine tetraacetic acid (EDTA) anti-coagulant. Heparin anti-coagulation is not recommended because of the tendency to form clots on storage. Samples which are not analyzed immediately should be stored at room temperature or in a refrigerator and assayed within 7 days; see assay instructions for specifics. If samples are to be kept longer they should be deep frozen at -20° C. One study showed drug recovery >90% for samples stored at -20° C for 6 months, with reduced recovery observed after 6 months.

2.7 Preparation for Intravenous Product

Prograf injection must be diluted with 0.9% Sodium Chloride Injection or 5% Dextrose Injection to a concentration between 0.004 mg/mL and 0.02 mg/mL prior to use. Diluted infusion solution should be stored in glass or polyethylene containers and should be discarded after 24 hours. The diluted infusion solution should not be stored in a PVC container due to decreased stability and the potential for extraction of phthalates. In situations where more dilute solutions are utilized (e.g., pediatric dosing, etc.), PVC-free tubing should likewise be used to minimize the potential for significant drug adsorption onto the tubing.

Parenteral drug products should be inspected visually for particulate matter and discoloration prior to administration, whenever solution and container permit.

Due to the chemical instability of tacrolimus in alkaline media, Prograf injection should not be mixed or co-infused with solutions of pH 9 or greater (e.g., ganciclovir or acyclovir).

3 DOSAGE FORMS AND STRENGTHS

• Oblong, hard capsule for oral administration contains anhydrous tacrolimus USP as follows:

° 0.5 mg, light-yellow color, imprinted in red “0.5 mg” on the capsule cap and “logo607”* on capsule body

° 1 mg, white color, imprinted in red “1 mg” on the capsule cap and “logo617”* on capsule body

° 5 mg, grayish-red color, imprinted with white “5 mg” on the capsule cap and “logo657”* on capsule body
*The logo is a letter 'f' in a box as shown on the capsules --

• 1 mL ampule for IV infusion contains anhydrous tacrolimus USP as follows:

° 5 mg/mL, sterile solution

4 CONTRAINDICATIONS

Prograf is contraindicated in patients with a hypersensitivity to tacrolimus. Prograf injection is contraindicated in patients with a hypersensitivity to HCO-60 (polyoxyl 60 hydrogenated castor oil). Hypersensitivity symptoms reported include dyspnea, rash, pruritus, and acute respiratory distress syndrome [see Adverse Reactions (6)].

5 WARNINGS AND PRECAUTIONS

5.1 Management of Immunosuppression

Only physicians experienced in immunosuppressive therapy and management of organ transplant patients should use Prograf. Patients receiving the drug should be managed in facilities equipped and staffed with adequate laboratory and supportive medical resources. The physicians responsible for maintenance therapy should have complete information requisite for the follow up of the patient [see Boxed Warning].

5.2 Lymphoma and Other Malignancies

Patients receiving immunosuppressants, including Prograf, are at increased risk of developing lymphomas and other malignancies, particularly of the skin [see Boxed Warning]. The risk appears to be related to the intensity and duration of immunosuppression rather than to the use of any specific agent.

As usual for patients with increased risk for skin cancer, exposure to sunlight and UV light should be limited by wearing protective clothing and using a sunscreen with a high protection factor.

Post transplant lymphoproliferative disorder (PTLD) has been reported in immunosuppressed organ transplant recipients. The majority of PTLD events appear related to Epstein Barr Virus (EBV) infection. The risk of PTLD appears greatest in those individuals who are EBV seronegative, a population which includes many young children.

5.3 Serious Infections

Patients receiving immunosuppressants, including Prograf, are at increased risk of developing bacterial, viral, fungal, and protozoal infections, including opportunistic infections [see Boxed Warning and Warnings and Precautions (5.4, 5.5)]. These infections may lead to serious, including fatal, outcomes. Because of the danger of oversuppression of the immune system which can increase susceptibility to infection, combination immunosuppressant therapy should be used with caution.

5.4 Polyoma Virus Infections

Patients receiving immunosuppressants, including Prograf, are at increased risk for opportunistic infections, including polyoma virus infections. Polyoma virus infections in transplant patients may have serious, and sometimes fatal, outcomes. These include polyoma virus-associated nephropathy (PVAN), mostly due to BK virus infection, and JC virus-associated progressive multifocal leukoencephalopathy (PML) which have been observed in patients receiving tacrolimus [see Adverse Reactions (6.2)].

PVAN is associated with serious outcomes, including deteriorating renal function and kidney graft loss [see Adverse Reactions (6.2)]. Patient monitoring may help detect patients at risk for PVAN.

Cases of PML have been reported in patients treated with Prograf. PML, which is sometimes fatal, commonly presents with hemiparesis, apathy, confusion, cognitive deficiencies and ataxia. Risk factors for PML include treatment with immunosuppressant therapies and impairment of immune function. In immunosuppressed patients, physicians should consider PML in the differential diagnosis in patients reporting neurological symptoms and consultation with a neurologist should be considered as clinically indicated.

Reductions in immunosuppression should be considered for patients who develop evidence of PVAN or PML. Physicians should also consider the risk that reduced immunosuppression represents to the functioning allograft.

5.5 Cytomegalovirus (CMV) Infections

Patients receiving immunosuppressants, including Prograf, are at increased risk of developing CMV viremia and CMV disease. The risk of CMV disease is highest among transplant recipients seronegative for CMV at time of transplant who receive a graft from a CMV seropositive donor. Therapeutic approaches to limiting CMV disease exist and should be routinely provided. Patient monitoring may help detect patients at risk for CMV disease. Consideration should be given to reducing the amount of immunosuppression in patients who develop CMV viremia and/or CMV disease.

5.6 New Onset Diabetes After Transplant

Prograf was shown to cause new onset diabetes mellitus in clinical trials of kidney, liver, and heart transplantation. New onset diabetes after transplantation may be reversible in some patients. Black and Hispanic kidney transplant patients are at an increased risk. Blood glucose concentrations should be monitored closely in patients using Prograf [see Adverse Reactions (6.1)].

5.7 Nephrotoxicity

Prograf, like other calcineurin-inhibitors, can cause acute or chronic nephrotoxicity, particularly when used in high doses. Acute nephrotoxicity is most often related to vasoconstriction of the afferent renal arteriole, is characterized by increasing serum creatinine, hyperkalemia, and/or a decrease in urine output, and is typically reversible. Chronic calcineurin-inhibitor nephrotoxicity is associated with increased serum creatinine, decreased kidney graft life, and characteristic histologic changes observed on renal biopsy; the changes associated with chronic calcineurin-inhibitor nephrotoxicity are typically progressive. Patients with impaired renal function should be monitored closely as the dosage of Prograf may need to be reduced. In patients with persistent elevations of serum creatinine who are unresponsive to dosage adjustments, consideration should be given to changing to another immunosuppressive therapy.

Based on reported adverse reactions terms related to decreased renal function, nephrotoxicity was reported in approximately 52% of kidney transplantation patients and in 40% and 36% of liver transplantation patients receiving Prograf in the U.S. and European randomized trials, respectively, and in 59% of heart transplantation patients in a European randomized trial [see Adverse Reactions (6.1)].

Due to the potential for additive or synergistic impairment of renal function, care should be taken when administering Prograf with drugs that may be associated with renal dysfunction. These include, but are not limited to, aminoglycosides, ganciclovir, amphotericin B, cisplatin, nucleotide reverse transcriptase inhibitors (e.g., tenofovir) and protease inhibitors (e.g., ritonavir, indinavir). Similarly, care should be exercised when administering with CYP3A4 inhibitors such as antifungal drugs (e.g., ketoconazole), calcium channel blockers (e.g., diltiazem, verapamil), and macrolide antibiotics (e.g., clarithromycin, erythromycin, troleandomycin) which will result in increased tacrolimus whole blood concentrations due to inhibition of tacrolimus metabolism [see Drug Interactions (7.3, 7.4, 7.5, 7.6)].

5.8 Neurotoxicity

Prograf may cause a spectrum of neurotoxicities, particularly when used in high doses. The most severe neurotoxicities include posterior reversible encephalopathy syndrome (PRES), delirium, and coma. Patients treated with tacrolimus have been reported to develop PRES. Symptoms indicating PRES include headache, altered mental status, seizures, visual disturbances and hypertension. Diagnosis may be confirmed by radiological procedure. If PRES is suspected or diagnosed, blood pressure control should be maintained and immediate reduction of immunosuppression is advised. This syndrome is characterized by reversal of symptoms upon reduction or discontinuation of immunosuppression.

Coma and delirium, in the absence of PRES, have also been associated with high plasma concentrations of tacrolimus. Seizures have occurred in adult and pediatric patients receiving Prograf [see Adverse Reactions (6.1)].

Less severe neurotoxicities, include tremors, paresthesias, headache, and other changes in motor function, mental status, and sensory function [see Adverse Reactions (6.1)]. Tremor and headache have been associated with high whole-blood concentrations of tacrolimus and may respond to dosage adjustment.

5.9 Hyperkalemia

Hyperkalemia has been reported with Prograf use. Serum potassium levels should be monitored. Careful consideration should be given prior to use of other agents also associated with hyperkalemia (e.g., potassium-sparing diuretics, ACE inhibitors, angiotensin receptor blockers) during Prograf therapy [see Adverse Reactions (6.1)].

5.10 Hypertension

Hypertension is a common adverse effect of Prograf therapy and may require antihypertensive therapy [see Adverse Reactions (6.1)]. The control of blood pressure can be accomplished with any of the common antihypertensive agents, though careful consideration should be given prior to use of antihypertensive agents associated with hyperkalemia (e.g., potassium-sparing diuretics, ACE inhibitors, angiotensin receptor blockers) [see Warnings and Precautions (5.9)]. Calcium-channel blocking agents may increase tacrolimus blood concentrations and therefore require dosage reduction of Prograf [see Drug Interactions (7.5)].

5.11 Anaphylactic Reactions with Prograf Injection

Anaphylactic reactions have occurred with injectables containing castor oil derivatives, including Prograf, in a small percentage of patients (0.6%). The exact cause of these reactions is not known. Prograf injection should be reserved for patients who are unable to take Prograf capsules [see Indications and Usage (1.4)].

Patients receiving Prograf injection should be under continuous observation for at least the first 30 minutes following the start of the infusion and at frequent intervals thereafter. If signs or symptoms of anaphylaxis occur, the infusion should be stopped. An aqueous solution of epinephrine should be available at the bedside as well as a source of oxygen.

5.12 Use with Sirolimus

The safety and efficacy of Prograf with sirolimus has not been established in kidney transplant patients.

Use of sirolimus with Prograf in studies of de novo liver transplant patients was associated with an excess mortality, graft loss, and hepatic artery thrombosis (HAT) and is not recommended [see Indications and Usage (1.4)].

Use of sirolimus (2 mg per day) with Prograf in heart transplant patients in a U.S. trial was associated with increased risk of renal function impairment, wound healing complications, and insulin-dependent post-transplant diabetes mellitus, and is not recommended [see Clinical Studies (14.3)].

5.13 Use with CYP3A4 Inhibitors and Inducers

When coadministering Prograf with strong CYP3A4-inhibitors (e.g., telaprevir, boceprevir, ritonavir, ketoconazole, itraconazole, voriconazole, clarithromycin) and strong inducers (e.g., rifampin, rifabutin) adjustments in the dosing regimen of Prograf and subsequent frequent monitoring of tacrolimus whole blood trough concentrations and tacrolimus-associated adverse reactions are recommended [see Drug Interactions (7)].

5.14 QT Prolongation

Prograf may prolong the QT/QTc interval and may cause Torsade de Pointes. Avoid Prograf in patients with congenital long QT syndrome. In patients with congestive heart failure, bradyarrhythmias, those taking certain antiarrhythmic medications or other medicinal products that lead to QT prolongation, and those with electrolyte disturbances such as hypokalemia, hypocalcemia, or hypomagnesemia, consider obtaining electrocardiograms and monitoring electrolytes (magnesium, potassium, calcium) periodically during treatment.

When coadministering Prograf with other substrates and/or inhibitors of CYP3A4 that also have the potential to prolong the QT interval, a reduction in Prograf dose, frequent monitoring of tacrolimus whole blood concentrations, and monitoring for QT prolongation is recommended. Use of Prograf with amiodarone has been reported to result in increased tacrolimus whole blood concentrations with or without concurrent QT prolongation [see Drug Interactions (7)].

5.15 Myocardial Hypertrophy

Myocardial hypertrophy has been reported in infants, children, and adults, particularly those with high tacrolimus trough concentrations, and is generally manifested by echocardiographically demonstrated concentric increases in left ventricular posterior wall and interventricular septum thickness. This condition appears reversible in most cases following dose reduction or discontinuance of therapy. In patients who develop renal failure or clinical manifestations of ventricular dysfunction while receiving Prograf therapy, echocardiographic evaluation should be considered. If myocardial hypertrophy is diagnosed, dosage reduction or discontinuation of Prograf should be considered [see Adverse Reactions (6.2)].

5.16 Immunizations

The use of live vaccines should be avoided during treatment with tacrolimus; examples include (not limited to) the following: intranasal influenza, measles, mumps, rubella, oral polio, BCG, yellow fever, varicella, and TY21a typhoid vaccines.

5.17 Pure Red Cell Aplasia

Cases of pure red cell aplasia (PRCA) have been reported in patients treated with tacrolimus. A mechanism for tacrolimus-induced PRCA has not been elucidated. All patients reported risk factors for PRCA such as parvovirus B19 infection, underlying disease, or concomitant medications associated with PRCA. If PRCA is diagnosed, discontinuation of Prograf should be considered [see Adverse Reactions (6.2)].

5.18 Gastrointestinal Perforation

Gastrointestinal perforation has been reported in patients treated with Prograf; all reported cases were considered to be a complication of transplant surgery or accompanied by infection, diverticulum, or malignant neoplasm. As gastrointestinal perforation may be serious or life-threatening, appropriate medical/surgical management should be instituted promptly [see Adverse Reactions (6.1)].

6 ADVERSE REACTIONS

The following serious and otherwise important adverse drug reactions are discussed in greater detail in other sections of labeling:

- Lymphoma and Other Malignancies [see Boxed Warning, Warnings and Precautions (5.2)]
- Serious Infections [see Boxed Warning, Warnings and Precautions (5.3)]
- Polyoma Virus Infections [see Boxed Warning, Warnings and Precautions (5.4)]
- CMV Infections [see Boxed Warning, Warnings and Precautions (5.5)]
- New Onset Diabetes After Transplant [see Warnings and Precautions (5.6)]
- Nephrotoxicity [see Warnings and Precautions (5.7)]
- Neurotoxicity [see Warnings and Precautions (5.8)]
- Hyperkalemia [see Warnings and Precautions (5.9)]
- Hypertension [see Warnings and Precautions (5.10)]
- Anaphylaxis with Prograf Injection [see Warnings and Precautions (5.11)]
- Myocardial Hypertrophy [see Warnings and Precautions (5.15)]
- Pure Red Cell Aplasia [see Warnings and Precautions (5.17)]
- Gastrointestinal Perforation [see Warnings and Precautions (5.18)]

6.1 Clinical Studies Experience

Because clinical trials are conducted under widely varying conditions, adverse reaction rates observed in the clinical trials of a drug cannot be directly compared to rates in the clinical trials of another drug and may not reflect the rates observed in practice. In addition, the clinical trials were not designed to establish comparative differences across study arms with regards to the adverse reactions discussed below.

Kidney Transplant

The incidence of adverse reactions was determined in three randomized kidney transplant trials. One of the trials used azathioprine (AZA) and corticosteroids and two of the trials used mycophenolate mofetil (MMF) and corticosteroids concomitantly for maintenance immunosuppression.

Prograf-based immunosuppression in conjunction with azathioprine and corticosteroids following kidney transplantation was assessed in trial where 205 patients received Prograf based immunosuppression and 207 patients received cyclosporine based immunosuppression. The trial population had a mean age of 43 years (mean±sd was 43±13 years on Prograf and 44±12 years on cyclosporine arm), the distribution was 61% male, and the composition was White (58%), Black (25%), Hispanic (12%) and Other (5%). The 12 month post-transplant information from this trial is presented below.

The most common adverse reactions (≥ 30%) observed in Prograf-treated kidney transplant patients are: infection, tremor, hypertension, abnormal renal function, constipation, diarrhea, headache, abdominal pain, insomnia, nausea, hypomagnesemia, urinary tract infection, hypophosphatemia, peripheral edema, asthenia, pain, hyperlipidemia, hyperkalemia and anemia.

Adverse reactions that occurred in ≥ 15% of kidney transplant patients treated with Prograf in conjunction with azathioprine are presented below:

Table 4. Kidney Transplantation: Adverse Reactions Occurring in ≥ 15% of Patients Treated with Prograf in Conjunction with Azathioprine (AZA)
 | Prograf/AZA; (N=205) | Cyclosporine/AZA (N=207)
Nervous System
Tremor; Headache; Insomnia; Paresthesia; Dizziness | 54%; 44%; 32%; 23%; 19% | 34%; 38%; 30%; 16%; 16%
Gastrointestinal
Diarrhea; Nausea; Constipation; Vomiting; Dyspepsia | 44%; 38%; 35%; 29%; 28% | 41%; 36%; 43%; 23%; 20%
Cardiovascular
Hypertension; Chest Pain | 50%; 19% | 52%; 13%
Urogenital
Creatinine Increased; Urinary Tract Infection | 45%; 34% | 42%; 35%
Metabolic and Nutritional
Hypophosphatemia; Hypomagnesemia; Hyperlipemia; Hyperkalemia; Diabetes Mellitus; Hypokalemia; Hyperglycemia; Edema | 49%; 34%; 31%; 31%; 24%; 22%; 22%; 18% | 53%; 17%; 38%; 32%; 9%; 25%; 16%; 19%
Hemic and Lymphatic
Anemia; Leukopenia | 30%; 15% | 24%; 17%
Miscellaneous
Infection; Peripheral Edema; Asthenia; Abdominal Pain; Pain; Fever; Back Pain | 45%; 36%; 34%; 33%; 32%; 29%; 24% | 49%; 48%; 30%; 31%; 30%; 29%; 20%
Respiratory System
Dyspnea; Cough Increased | 22%; 18% | 18%; 15%
Musculoskeletal
Arthralgia | 25% | 24%
Skin
Rash; Pruritus | 17%; 15% | 12%; 7%

Two trials were conducted for Prograf-based immunosuppression in conjunction with MMF and corticosteroids. In the non-US trial (Study 1), the incidence of adverse reactions was based on 1195 kidney transplant patients that received Prograf (Group C, n=403), or one of two cyclosporine (CsA) regimens (Group A, n=384 and Group B, n=408) in combination with MMF and corticosteroids; all patients, except those in one of the two cyclosporine groups, also received induction with daclizumab. The trial population had a mean age of 46 years (range 17 to 76), the distribution was 65% male, and the composition was 93% Caucasian. The 12 month post-transplant information from this trial is presented below.

Adverse reactions that occurred in ≥ 10% of kidney transplant patients treated with Prograf in conjunction with MMF in Study 1 [Note: This trial was conducted entirely outside of the United States. Such trials often report a lower incidence of adverse reactions in comparison to U.S. trials] are presented below:

Table 5. Kidney Transplantation: Adverse Reactions Occurring in ≥ 10% of Patients Treated with Prograf in Conjunction with MMF (Study 1)
 | Prograf (Group C) | Cyclosporine (Group A) | Cyclosporine (Group B)
 | (N=403) | (N=384) | (N=408)
Diarrhea | 25% | 16% | 13%
Urinary Tract Infection | 24% | 28% | 24%
Anemia | 17% | 19% | 17%
Hypertension | 13% | 14% | 12%
Leukopenia | 13% | 10% | 10%
Edema Peripheral | 11% | 12% | 13%
Hyperlipidemia | 10% | 15% | 13%
Key: Group A = CsA/MMF/CS, B = CsA/MMF/CS/Daclizumab, C= Tac/MMF/CS/Daclizumab
CsA= Cyclosporine, CS = Corticosteroids, Tac = Tacrolimus, MMF = mycophenolate mofetil

In the U.S. trial (Study 2) with Prograf-based immunosuppression in conjunction with MMF and corticosteroids, 424 kidney transplant patients received Prograf (n=212) or cyclosporine (n=212) in combination with MMF 1 gram twice daily, basiliximab induction, and corticosteroids. The trial population had a mean age of 48 years (range 17 to 77), the distribution was 63% male, and the composition was White (74%), Black (20%), Asian (3%) and other (3%). The 12 month post-transplant information from this trial is presented below.

Adverse reactions that occurred in ≥15% of kidney transplant patients treated with Prograf in conjunction with MMF in Study 2 are presented below:

Table 6. Kidney Transplantation: Adverse Reactions Occurring in ≥ 15% of Patients Treated with Prograf in Conjunction with MMF (Study 2)
 | Prograf/MMF | Cyclosporine/MMF
 | (N=212) | (N=212)
Gastrointestinal Disorders
Diarrhea | 44% | 26%
Nausea | 39% | 47%
Constipation | 36% | 41%
Vomiting | 26% | 25%
Dyspepsia | 18% | 15%
Injury, Poisoning, and Procedural Complications
Post-Procedural Pain | 29% | 27%
Incision Site Complication | 28% | 23%
Graft Dysfunction | 24% | 18%
Metabolism and Nutrition Disorders
Hypomagnesemia | 28% | 22%
Hypophosphatemia | 28% | 21%
Hyperkalemia | 26% | 19%
Hyperglycemia | 21% | 15%
Hyperlipidemia | 18% | 25%
Hypokalemia | 16% | 18%
Nervous System Disorders
Tremor | 34% | 20%
Headache | 24% | 25%
Blood and Lymphatic System Disorders
Anemia | 30% | 28%
Leukopenia | 16% | 12%
Miscellaneous
Edema Peripheral | 35% | 46%
Hypertension | 32% | 35%
Insomnia | 30% | 21%
Urinary Tract Infection | 26% | 22%
Blood Creatinine Increased | 23% | 23%

Less frequently observed adverse reactions in both liver transplantation and kidney transplantation patients are described under the subsection Less Frequently Reported Adverse Reactions.
Liver Transplantation

There were two randomized comparative liver transplant trials. In the U.S. trial, 263 adult and pediatric patients received tacrolimus and steroids and 266 patients received cyclosporine-based immunosuppressive regimen (CsA/AZA). The trial population had a mean age of 44 years (range 0.4 to70), the distribution was 52% male, and the composition was White (78%), Black (5%), Asian (2%), Hispanic (13%) and Other (2%). In the European trial, 270 patients received tacrolimus and steroids and 275 patients received CsA/AZA. The trial population had a mean age of 46 years (range 15 to 68), the distribution was 59% male, and the composition was White (95.4%), Black (1%), Asian (2%) and Other (2%).

The proportion of patients reporting more than one adverse event was > 99% in both the tacrolimus group and the CsA/AZA group. Precautions must be taken when comparing the incidence of adverse reactions in the U.S. trial to that in the European trial. The 12-month post-transplant information from the U.S. trial and from the European trial is presented below. The two trials also included different patient populations and patients were treated with immunosuppressive regimens of differing intensities. Adverse reactions reported in ≥15% in tacrolimus patients (combined trial results) are presented below for the two controlled trials in liver transplantation.

The most common adverse reactions (≥ 40%) observed in Prograf-treated liver transplant patients are: tremor, headache, diarrhea, hypertension, nausea, abnormal renal function, abdominal pain, insomnia, paresthesia, anemia, pain, fever, asthenia, hyperkalemia, hypomagnesemia, and hyperglycemia. These all occur with oral and IV administration of Prograf and some may respond to a reduction in dosing (e.g., tremor, headache, paresthesia, hypertension). Diarrhea was sometimes associated with other gastrointestinal complaints such as nausea and vomiting.

Table 7. Liver Transplantation: Adverse Reactions Occurring in ≥ 15% of Patients Treated with Prograf
 | U.S. TRIAL |  | EUROPEAN TRIAL
 | Prograf; (N=250) | Cyclosporine/AZA (N=250) | Prograf; (N=264) | Cyclosporine/AZA (N=265)
Nervous System
Headache; Insomnia; Tremor; Paresthesia | 64%; 64%; 56%; 40% | 60%; 68%; 46%; 30% | 37%; 32%; 48%; 17% | 26%; 23%; 32%; 17%
Gastrointestinal
Diarrhea; Nausea; LFT Abnormal; Anorexia; Vomiting; Constipation | 72%; 46%; 36%; 34%; 27%; 24% | 47%; 37%; 30%; 24%; 15%; 27% | 37%; 32%; 6%; 7%; 14%; 23% | 27%; 27%; 5%; 5%; 11%; 21%
Cardiovascular
Hypertension | 47% | 56% | 38% | 43%
Urogenital
Kidney Function Abnormal | 40% | 27% | 36% | 23%
Creatinine Increased | 39% | 25% | 24% | 19%
BUN Increased | 30% | 22% | 12% | 9%
Oliguria | 18% | 15% | 19% | 12%
Urinary Tract Infection | 16% | 18% | 21% | 19%
Metabolic and Nutritional
Hypomagnesemia; Hyperglycemia; Hyperkalemia; Hypokalemia | 48%; 47%; 45%; 29% | 45%; 38%; 26%; 34% | 16%; 33%; 13%; 13% | 9%; 22%; 9%; 16%
Hemic and Lymphatic
Anemia; Leukocytosis; Thrombocytopenia | 47%; 32%; 24% | 38%; 26%; 20% | 5%; 8%; 14% | 1%; 8%; 19%
Miscellaneous
Pain; Abdominal Pain; Asthenia; Fever; Back Pain; Ascites; Peripheral Edema | 63%; 59%; 52%; 48%; 30%; 27%; 26% | 57%; 54%; 48%; 56%; 29%; 22%; 26% | 24%; 29%; 11%; 19%; 17%; 7%; 12% | 22%; 22%; 7%; 22%; 17%; 8%; 14%
Respiratory System
Pleural Effusion; Dyspnea; Atelectasis | 30%; 29%; 28% | 32%; 23%; 30% | 36%; 5%; 5% | 35%; 4%; 4%
Skin and Appendages
Pruritus; Rash | 36%; 24% | 20%; 19% | 15%; 10% | 7%; 4%

Less frequently observed adverse reactions in both liver transplantation and kidney transplantation patients are described under the subsection Less Frequently Reported Adverse Reactions.
Heart Transplantation

The incidence of adverse reactions was determined based on two trials in primary orthotopic heart transplantation. In a trial conducted in Europe, 314 patients received a regimen of antibody induction, corticosteroids and azathioprine (AZA) in combination with Prograf (n=157) or cyclosporine (n=157) for 18 months. The trial population had a mean age of 51 years (range 18 to 65), the distribution was 82% male, and the composition was White (96%), Black (3%) and other (1%).

The most common adverse reactions (≥ 15%) observed in Prograf-treated heart transplant patients are: abnormal renal function, hypertension, diabetes mellitus, CMV infection, tremor, hyperglycemia, leukopenia, infection, anemia, bronchitis, pericardial effusion, urinary tract infection and hyperlipemia.

Adverse reactions in heart transplant patients in the European trial are presented below:

Table 8. Heart Transplantation: Adverse Reactions Occurring in ≥ 15% of Patients Treated with Prograf in Conjunction with Azathioprine (AZA)
 | Prograf/AZA; (n=157) | Cyclosporine/AZA; (n=157)
Cardiovascular System
Hypertension | 62% | 69%
Pericardial Effusion | 15% | 14%
Body as a Whole
CMV Infection | 32% | 30%
Infection | 24% | 21%
Metabolic and Nutritional Disorders
Diabetes Mellitus | 26% | 16%
Hyperglycemia | 23% | 17%
Hyperlipemia | 18% | 27%
Hemic and Lymphatic System
Anemia | 50% | 36%
Leukopenia | 48% | 39%
Urogenital System
Kidney Function Abnormal | 56% | 57%
Urinary Tract Infection | 16% | 12%
Respiratory System
Bronchitis | 17% | 18%
Nervous System
Tremor | 15% | 6%

In the European trial, the cyclosporine trough concentrations were above the pre-defined target range (i.e., 100 to 200 ng/mL) at Day 122 and beyond in 32 to 68% of the patients in the cyclosporine treatment arm, whereas the tacrolimus trough concentrations were within the pre-defined target range (i.e., 5 to 15 ng/mL) in 74 to 86% of the patients in the tacrolimus treatment arm.

In a U.S. trial, the incidence of adverse reactions was based on 331 heart transplant patients that received corticosteroids and Prograf in combination with sirolimus (n=109), Prograf in combination with MMF (n=107) or cyclosporine modified in combination with MMF (n=115) for 1 year. The trial population had a mean age of 53 years (range 18 to 75), the distribution was 78% male, and the composition was White (83%), Black (13%) and other (4%).

Only selected targeted treatment-emergent adverse reactions were collected in the U.S. heart transplantation trial. Those reactions that were reported at a rate of 15% or greater in patients treated with Prograf and MMF include the following: any target adverse reactions (99%), hypertension (89%), hyperglycemia requiring antihyperglycemic therapy (70%), hypertriglyceridemia (65%), anemia (hemoglobin <10.0 g/dL) (65%), fasting blood glucose >140 mg/dL (on two separate occasions) (61%), hypercholesterolemia (57%), hyperlipidemia (34%), WBCs <3000 cells/mcL (34%), serious bacterial infections (30%), magnesium <1.2 mEq/L (24%), platelet count <75,000 cells/mcL (19%), and other opportunistic infections (15%).

Other targeted treatment-emergent adverse reactions in Prograf-treated patients occurred at a rate of less than 15%, and include the following: Cushingoid features, impaired wound healing, hyperkalemia, Candida infection, and CMV infection/syndrome.

New Onset Diabetes After Transplant

Kidney Transplant

New Onset Diabetes After Transplant (NODAT) is defined as a composite of fasting plasma glucose ≥126 mg/dL, HbA1C ≥ 6%, insulin use ≥ 30 days or oral hypoglycemic use. In a trial in kidney transplant patients (Study 2), NODAT was observed in 75% in the Prograf-treated and 61% in the Neoral-treated patients without pre-transplant history of diabetes mellitus (Table 9) [see Clinical Studies (14.1)].

Table 9. Incidence of New Onset Diabetes After Transplant at 1 year in Kidney Transplant Recipients in a Phase 3 Trial (Study 2)
Parameter | Treatment Group
Parameter | Prograf/MMF; (n = 212) | Neoral/MMF; (n = 212)
NODAT | 112/150 (75%) | 93/152 (61%)
Fasting Plasma Glucose ≥ 126 mg/dL | 96/150 (64%) | 80/152 (53%)
HbA1C ≥ 6% | 59/150 (39%) | 28/152 (18%)
Insulin Use ≥ 30 days | 9/150 (6%) | 4/152 (3%)
Oral Hypoglycemic Use | 15/150 (10%) | 5/152 (3%)

In early trials of Prograf, Post-Transplant Diabetes Mellitus (PTDM) was evaluated with a more limited criteria of “use of insulin for 30 or more consecutive days with < 5 day gap” in patients without a prior history of insulin-dependent diabetes mellitus or non-insulin dependent diabetes mellitus. Data are presented in Tables 10 to 13. PTDM was reported in 20% of Prograf/Azathioprine (AZA)-treated kidney transplant patients without pre-transplant history of diabetes mellitus in a Phase 3 trial (Table 10). The median time to onset of PTDM was 68 days. Insulin dependence was reversible in 15% of these PTDM patients at one year and in 50% at 2 years post-transplant. Black and Hispanic kidney transplant patients were at an increased risk of development of PTDM (Table 11).

Table 10. Incidence of Post-Transplant Diabetes Mellitus and Insulin Use at 2 Years in Kidney Transplant Recipients in a Phase 3 Trial using Azathioprine (AZA)
Status of PTDM [Use of insulin for 30 or more consecutive days, with < 5 day gap, without a prior history of insulin-dependent diabetes mellitus or non-insulin dependent diabetes mellitus.] | Prograf/AZA | CsA/AZA
Patients without pre-transplant history of diabetes mellitus | 151 | 151
New onset PTDM, 1st Year | 30/151 (20%) | 6/151 (4%)
Still insulin-dependent at one year in those without prior history of diabetes | 25/151 (17%) | 5/151 (3%)
New onset PTDM post 1 year | 1 | 0
Patients with PTDM at 2 years | 16/151 (11%) | 5/151 (3%)

Table 11. Development of Post-Transplant Diabetes Mellitus by Race or Ethnicity and by Treatment Group During First Year Post Kidney Transplantation in a Phase 3 Trial
Patient Race | Patients Who Developed PTDM [Use of insulin for 30 or more consecutive days, with < 5 day gap, without a prior history of insulin-dependent diabetes mellitus or non-insulin dependent diabetes mellitus.]
Patient Race | Prograf | Cyclosporine
Black | 15/41 (37%) | 3 (8%)
Hispanic | 5/17 (29%) | 1 (6%)
Caucasian | 10/82 (12%) | 1 (1%)
Other | 0/11 (0%) | 1 (10%)
Total | 30/151 (20%) | 6 (4%)

Liver Transplant

Insulin-dependent PTDM was reported in 18% and 11% of Prograf-treated liver transplant patients and was reversible in 45% and 31% of these patients at 1 year post-transplant, in the U.S. and European randomized trials, respectively, (Table 12). Hyperglycemia was associated with the use of Prograf in 47% and 33% of liver transplant recipients in the U.S. and European randomized trials, respectively, and may require treatment [see Adverse Reactions (6.1)].

Table 12. Incidence of Post-Transplant Diabetes Mellitus and Insulin Use at 1 Year in Liver Transplant Recipients
Status of PTDM [Use of insulin for 30 or more consecutive days, with < 5 day gap, without a prior history of insulin-dependent diabetes mellitus or non-insulin dependent diabetes mellitus.] | US Trial |  | European Trial
Status of PTDM [Use of insulin for 30 or more consecutive days, with < 5 day gap, without a prior history of insulin-dependent diabetes mellitus or non-insulin dependent diabetes mellitus.] | Prograf | Cyclosporine | Prograf | Cyclosporine
Patients at risk [Patients without pre-transplant history of diabetes mellitus.] | 239 | 236 | 239 | 249
New Onset PTDM | 42 (18%) | 30 (13%) | 26 (11%) | 12 (5%)
Patients still on insulin at 1 year | 23 (10%) | 19 (8%) | 18 (8%) | 6 (2%)

Heart Transplant

Insulin-dependent PTDM was reported in 13% and 22% of Prograf-treated heart transplant patients receiving mycophenolate mofetil (MMF) or azathioprine (AZA) and was reversible in 30% and 17% of these patients at one year post-transplant, in the U.S. and European randomized trials, respectively (Table 13). Hyperglycemia defined as two fasting plasma glucose levels ≥126 mg/dL was reported with the use of Prograf plus MMF or AZA in 32% and 35% of heart transplant recipients in the U.S. and European randomized trials, respectively, and may require treatment [see Adverse Reactions (6.1)].

Table 13. Incidence of Post-Transplant Diabetes Mellitus and Insulin Use at 1 Year in Heart Transplant Recipients
Status of PTDM [Use of insulin for 30 or more consecutive days without a prior history of insulin-dependent diabetes mellitus or non-insulin dependent diabetes mellitus.] | US Trial |  | European Trial
Status of PTDM [Use of insulin for 30 or more consecutive days without a prior history of insulin-dependent diabetes mellitus or non-insulin dependent diabetes mellitus.] | Prograf/MMF | Cyclosporine/MMF | Prograf/AZA | Cyclosporine/AZA
Patients at risk [Patients without pre-transplant history of diabetes mellitus.] | 75 | 83 | 132 | 138
New Onset PTDM | 10 (13%) | 6 (7%) | 29 (22%) | 5 (4%)
Patients still on insulin at 1 year [7-12 months for the U.S. trial.] | 7 (9%) | 1 (1%) | 24 (18%) | 4 (3%)

Less Frequently Reported Adverse Reactions (>3% and <15%)

The following adverse reactions were reported in either liver, kidney, and/or heart transplant recipients who were treated with tacrolimus in clinical trials.
Nervous System [see Warnings and Precautions (5.8)]

Abnormal dreams, agitation, amnesia, anxiety, confusion, convulsion, crying, depression, elevated mood, emotional lability, encephalopathy, haemorrhagic stroke, hallucinations, hypertonia, incoordination, monoparesis, myoclonus, nerve compression, nervousness, neuralgia, neuropathy, paralysis flaccid, psychomotor skills impaired, psychosis, quadriparesis, somnolence, thinking abnormal, vertigo, writing impaired
Special Senses

Abnormal vision, amblyopia, ear pain, otitis media, tinnitus
Gastrointestinal

Cholangitis, cholestatic jaundice, duodenitis, dysphagia, esophagitis, flatulence, gastritis, gastroesophagitis, gastrointestinal hemorrhage, GGT increase, GI disorder, GI perforation, hepatitis, hepatitis granulomatous, ileus, increased appetite, jaundice, liver damage, oesophagitis ulcerative, oral moniliasis, pancreatic pseudocyst, rectal disorder, stomatitis
Cardiovascular

Abnormal ECG, angina pectoris, arrhythmia, atrial fibrillation, atrial flutter, bradycardia, cardiac fibrillation, cardiopulmonary failure, cardiovascular disorder, congestive heart failure, deep thrombophlebitis, echocardiogram abnormal, electrocardiogram QRS complex abnormal, electrocardiogram ST segment abnormal, heart failure, heart rate decreased, hemorrhage, hypotension, peripheral vascular disorder, phlebitis, postural hypotension, syncope, tachycardia, thrombosis, vasodilatation
Urogenital

Acute kidney failure [see Warnings and Precautions (5.7)], albuminuria, BK nephropathy, bladder spasm, cystitis, dysuria, hematuria, hydronephrosis, kidney failure, kidney tubular necrosis, nocturia, pyuria, toxic nephropathy, urge incontinence, urinary frequency, urinary incontinence, urinary retention, vaginitis
Metabolic/Nutritional

Acidosis, alkaline phosphatase increased, alkalosis, ALT (SGPT) increased, AST (SGOT) increased, bicarbonate decreased, bilirubinemia, dehydration, GGT increased, gout, healing abnormal, hypercalcemia, hypercholesterolemia, hyperphosphatemia, hyperuricemia, hypervolemia, hypocalcemia, hypoglycemia, hyponatremia, hypoproteinemia, lactic dehydrogenase increase, weight gain
Endocrine

Cushing’s syndrome
Hemic/Lymphatic

Coagulation disorder, ecchymosis, haematocrit increased, haemoglobin abnormal, hypochromic anemia, leukocytosis, polycythemia, prothrombin decreased, serum iron decreased
Miscellaneous

Abdomen enlarged, abscess, accidental injury, allergic reaction, cellulitis, chills, fall, feeling abnormal, flu syndrome, generalized edema, hernia, mobility decreased, peritonitis, photosensitivity reaction, sepsis, temperature intolerance, ulcer
Musculoskeletal

Arthralgia, cramps, generalized spasm, joint disorder, leg cramps, myalgia, myasthenia, osteoporosis
Respiratory

Asthma, emphysema, hiccups, lung disorder, lung function decreased, pharyngitis, pneumonia, pneumothorax, pulmonary edema, respiratory disorder, rhinitis, sinusitis, voice alteration
Skin

Acne, alopecia, exfoliative dermatitis, fungal dermatitis, herpes simplex, herpes zoster, hirsutism, neoplasm skin benign, skin discoloration, skin disorder, skin ulcer, sweating

6.2 Postmarketing Adverse Reactions

The following adverse reactions have been reported from worldwide marketing experience with Prograf. Because these reactions are reported voluntarily from a population of uncertain size it is not always possible to reliably estimate their frequency or establish a causal relationship to drug exposure. Decisions to include these reactions in labeling are typically based on one or more of the following factors: (1) seriousness of the reaction, (2) frequency of the reporting, or (3) strength of causal connection to the drug.

Other reactions include:
Cardiovascular

Atrial fibrillation, atrial flutter, cardiac arrhythmia, cardiac arrest, electrocardiogram T wave abnormal, flushing, myocardial infarction, myocardial ischaemia, pericardial effusion, QT prolongation, Torsade de Pointes, venous thrombosis deep limb, ventricular extrasystoles, ventricular fibrillation, myocardial hypertrophy [see Warnings and Precautions (5.15)].
Gastrointestinal

Bile duct stenosis, colitis, enterocolitis, gastroenteritis, gastrooesophageal reflux disease, hepatic cytolysis, hepatic necrosis, hepatotoxicity, impaired gastric emptying, liver fatty, mouth ulceration, pancreatitis haemorrhagic, pancreatitis necrotizing, stomach ulcer, venoocclusive liver disease
Hemic/Lymphatic

Agranulocytosis, disseminated intravascular coagulation, hemolytic anemia, neutropenia, pancytopenia, thrombocytopenic purpura, thrombotic thrombocytopenic purpura, pure red cell aplasia [see Warnings and Precautions (5.17)]
Infections

Cases of progressive multifocal leukoencephalopathy (PML), sometimes fatal; -polyoma virus-associated nephropathy, (PVAN) including graft loss [see Warnings and Precautions (5.4)]
Metabolic/Nutritional

Glycosuria, increased amylase including pancreatitis, weight decreased
Miscellaneous

Feeling hot and cold, feeling jittery, hot flushes, multi-organ failure, primary graft dysfunction
Nervous System

Carpal tunnel syndrome, cerebral infarction, hemiparesis, leukoencephalopathy, mental disorder, mutism, posterior reversible encephalopathy syndrome (PRES) [see Warnings and Precautions (5.8)], progressive multifocal leukoencephalopathy (PML) [see Warnings and Precautions (5.4)], quadriplegia, speech disorder, syncope
Respiratory

Acute respiratory distress syndrome, interstitial lung disease, lung infiltration, respiratory distress, respiratory failure
Skin

Stevens-Johnson syndrome, toxic epidermal necrolysis
Special Senses

Blindness, blindness cortical, hearing loss including deafness, photophobia
Urogenital

Acute renal failure, cystitis haemorrhagic, hemolytic-uremic syndrome, micturition disorder

7 DRUG INTERACTIONS

Since tacrolimus is metabolized mainly by CYP3A enzymes, drugs or substances known to inhibit these enzymes may increase tacrolimus whole blood concentrations. Drugs known to induce CYP3A enzymes may decrease tacrolimus whole blood concentrations [see Warnings and Precautions (5.13) and Clinical Pharmacology (12.3)]. Dose adjustments may be needed along with frequent monitoring of tacrolimus whole blood trough concentrations when Prograf is administered with CYP3A inhibitors or inducers. In addition, patients should be monitored for adverse reactions including changes in renal function and QT prolongation [see Warnings and Precautions (5.7) and (5.14)].

7.1 Mycophenolic Acid Products

With a given dose of mycophenolic acid (MPA) products, exposure to MPA is higher with Prograf co-administration than with cyclosporine co-administration because cyclosporine interrupts the enterohepatic recirculation of MPA while tacrolimus does not. Clinicians should be aware that there is also a potential for increased MPA exposure after crossover from cyclosporine to Prograf in patients concomitantly receiving MPA-containing products.

7.2 Grapefruit Juice

Grapefruit juice inhibits CYP3A-enzymes resulting in increased tacrolimus whole blood trough concentrations, and patients should avoid eating grapefruit or drinking grapefruit juice with tacrolimus [see Dosage and Administration (2.5)].

7.3 Protease Inhibitors

Most protease inhibitors inhibit CYP3A enzymes and may increase tacrolimus whole blood concentrations. It is recommended to avoid concomitant use of tacrolimus with nelfinavir unless the benefits outweigh the risks [see Clinical Pharmacology (12.3)]. Whole blood concentrations of tacrolimus are markedly increased when co-administered with telaprevir or with boceprevir [see Clinical Pharmacology (12.3)]. Monitoring of tacrolimus whole blood concentrations and tacrolimus-associated adverse reactions, and appropriate adjustments in the dosing regimen of tacrolimus are recommended when tacrolimus and protease inhibitors (e.g., ritonavir, telaprevir, boceprevir) are used concomitantly.

7.4 Antifungal Agents

Frequent monitoring of whole blood concentrations and appropriate dosage adjustments of tacrolimus are recommended when concomitant use of the following antifungal drugs with tacrolimus is initiated or discontinued [see Clinical Pharmacology (12.3)].

Azoles: Voriconazole, posaconazole, itraconazole, ketoconazole, fluconazole and clotrimazole inhibit CYP3A metabolism of tacrolimus and increase tacrolimus whole blood concentrations. When initiating therapy with voriconazole or posaconazole in patients already receiving tacrolimus, it is recommended that the tacrolimus dose be initially reduced to one-third of the original dose and the subsequent tacrolimus doses be adjusted based on the tacrolimus whole blood concentrations.

Caspofungin is an inducer of CYP3A and decreases whole blood concentrations of tacrolimus.

7.5 Calcium Channel Blockers

Verapamil, diltiazem, nifedipine, and nicardipine inhibit CYP3A metabolism of tacrolimus and may increase tacrolimus whole blood concentrations. Monitoring of whole blood concentrations and appropriate dosage adjustments of tacrolimus are recommended when these calcium channel blocking drugs and tacrolimus are used concomitantly.

7.6 Antibacterials

Erythromycin, clarithromycin, troleandomycin and chloramphenicol inhibit CYP3A metabolism of tacrolimus and may increase tacrolimus whole blood concentrations. Monitoring of blood concentrations and appropriate dosage adjustments of tacrolimus are recommended when these drugs and tacrolimus are used concomitantly.

7.7 Antimycobacterials

Rifampin [see Clinical Pharmacology (12.3)] and rifabutin are inducers of CYP3A enzymes and may decrease tacrolimus whole blood concentrations. Monitoring of whole blood concentrations and appropriate dosage adjustments of tacrolimus are recommended when these antimycobacterial drugs and tacrolimus are used concomitantly.

7.8 Anticonvulsants

Phenytoin, carbamazepine and phenobarbital induce CYP3A enzymes and may decrease tacrolimus whole blood concentrations. Monitoring of whole blood concentrations and appropriate dosage adjustments of tacrolimus are recommended when these drugs and tacrolimus are used concomitantly.

Concomitant administration of phenytoin with tacrolimus may also increase phenytoin plasma concentrations. Thus, frequent monitoring phenytoin plasma concentrations and adjusting the phenytoin dose as needed are recommended when tacrolimus and phenytoin are administered concomitantly.

7.9 St. John’s Wort (Hypericum perforatum)

St. John’s Wort induces CYP3A enzymes and may decrease tacrolimus whole blood concentrations. Monitoring of whole blood concentrations and appropriate dosage adjustments of tacrolimus are recommended when St. John’s Wort and tacrolimus are co-administered.

7.10 Gastric Acid Suppressors/Neutralizers

Lansoprazole and omeprazole, as CYP2C19 and CYP3A4 substrates, may potentially inhibit the CYP3A4 metabolism of tacrolimus and thereby substantially increase tacrolimus whole blood concentrations, especially in transplant patients who are intermediate or poor CYP2C19 metabolizers, as compared to those patients who are efficient CYP2C19 metabolizers.

Cimetidine may also inhibit the CYP3A4 metabolism of tacrolimus and thereby substantially increase tacrolimus whole blood concentrations.

Coadministration with magnesium and aluminum hydroxide antacids increase tacrolimus whole blood concentrations [see Clinical Pharmacology (12.3)]. Monitoring of whole blood concentrations and appropriate dosage adjustments of tacrolimus are recommended when these drugs and tacrolimus are used concomitantly.

7.11 Others

Bromocriptine, nefazodone, metoclopramide, danazol, ethinyl estradiol, amiodarone and methylprednisolone may inhibit CYP3A metabolism of tacrolimus and increase tacrolimus whole blood concentrations. Monitoring of blood concentrations and appropriate dosage adjustments of tacrolimus are recommended when these drugs and tacrolimus are co-administered.

8 USE IN SPECIFIC POPULATIONS

8.1 Pregnancy

Pregnancy Category C - There are no adequate and well-controlled studies in pregnant women. Tacrolimus is transferred across the placenta. The use of tacrolimus during pregnancy in humans has been associated with neonatal hyperkalemia and renal dysfunction. Tacrolimus given orally to pregnant rabbits at 0.5 to 4.3 times the clinical dose and pregnant rats at 0.8 to 6.9 times the clinical dose was associated with an increased incidence of fetal death in utero, fetal malformations (cardiovascular, skeletal, omphalocele, and gallbladder agenesis) and maternal toxicity. Prograf should be used during pregnancy only if the potential benefit to the mother justifies the potential risk to the fetus.

In pregnant rabbits, tacrolimus at oral doses of 0.32 and 1.0 mg/kg, 0.5 to 4.3 times the clinical dose range (0.075 – 0.2 mg/kg) based on body surface area, was associated with maternal toxicity as well as an increased incidence of abortions. At the 1 mg/kg dose, fetal rabbits showed an increased incidence of malformations (ventricular hypoplasia, interventricular septal defect, bulbous aortic arch, stenosis of ductus arteriosus, interrupted ossification of vertebral arch, vertebral and rib malformations, omphalocele, and gallbladder agenesis) and developmental variations. In pregnant rats, tacrolimus at oral doses of 3.2 mg/kg, 2.6 to 6.9 times the clinical dose range was associated with maternal toxicity, an increase in late resorptions, decreased numbers of live births, and decreased pup weight and viability. Tacrolimus, given orally to pregnant rats after organogenesis and during lactation at 1.0 and 3.2 mg/kg, 0.8 to 6.9 times the recommended clinical dose range was associated with reduced pup weights and pup viability (3.2 mg/kg only); among the high dose pups that died early, an increased incidence of kidney hydronephrosis was observed.

8.3 Nursing Mothers

Tacrolimus is excreted in human milk. As the effect of chronic exposure to tacrolimus in healthy infants is not established, patients maintained on Prograf should discontinue nursing taking into consideration importance of drug to the mother.

8.4 Pediatric Use

The safety and efficacy of Prograf in pediatric kidney and heart transplant patients have not been established. Successful liver transplants have been performed in pediatric patients (ages up to 16 years) using Prograf. Two randomized active-controlled trials of Prograf in primary liver transplantation included 56 pediatric patients. Thirty-one patients were randomized to Prograf-based and 25 to cyclosporine-based therapies. Additionally, a minimum of 122 pediatric patients were studied in an uncontrolled trial of tacrolimus in living related donor liver transplantation. Pediatric patients generally required higher doses of Prograf to maintain blood trough concentrations of tacrolimus similar to adult patients [see Dosage and Administration (2.2)].

8.5 Geriatric Use

Clinical trials of Prograf did not include sufficient numbers of subjects aged 65 and over to determine whether they respond differently from younger subjects. Other reported clinical experience has not identified differences in responses between the elderly and younger patients. In general, dose selection for an elderly patient should be cautious, usually starting at the low end of the dosing range, reflecting the greater frequency of decreased hepatic, renal, or cardiac function, and of concomitant disease or other drug therapy.

8.6 Use in Renal Impairment

The pharmacokinetics of Prograf in patients with renal impairment was similar to that in healthy volunteers with normal renal function. However, consideration should be given to dosing Prograf at the lower end of the therapeutic dosing range in patients who have received a liver or heart transplant and have pre-existing renal impairment. Further reductions in dose below the targeted range may be required [see Dosage and Administration (2.3) and Clinical Pharmacology (12.3)].

8.7 Use in Hepatic Impairment

The mean clearance of tacrolimus was substantially lower in patients with severe hepatic impairment (mean Child-Pugh score: >10) compared to healthy volunteers with normal hepatic function. Close monitoring of tacrolimus trough concentrations is warranted in patients with hepatic impairment [see Clinical Pharmacology (12.3)].

The use of Prograf in liver transplant recipients experiencing post-transplant hepatic impairment may be associated with increased risk of developing renal insufficiency related to high whole-blood trough concentrations of tacrolimus. These patients should be monitored closely and dosage adjustments should be considered. Some evidence suggests that lower doses should be used in these patients [see Dosage and Administration (2.3) and Clinical Pharmacology (12.3)].

10 OVERDOSAGE

Limited overdosage experience is available. Acute overdosages of up to 30 times the intended dose have been reported. Almost all cases have been asymptomatic and all patients recovered with no sequelae. Acute overdosage was sometimes followed by adverse reactions consistent with those listed in Adverse Reactions (6) (including tremors, abnormal renal function, hypertension, and peripheral edema); in one case of acute overdosage, transient urticaria and lethargy were observed. Based on the poor aqueous solubility and extensive erythrocyte and plasma protein binding, it is anticipated that tacrolimus is not dialyzable to any significant extent; there is no experience with charcoal hemoperfusion. The oral use of activated charcoal has been reported in treating acute overdoses, but experience has not been sufficient to warrant recommending its use. General supportive measures and treatment of specific symptoms should be followed in all cases of overdosage.

In acute oral and IV toxicity studies, mortalities were seen at or above the following doses: in adult rats, 52 times the recommended human oral dose; in immature rats, 16 times the recommended oral dose; and in adult rats, 16 times the recommended human IV dose (all based on body surface area corrections).

11 DESCRIPTION

Prograf is available for oral administration as capsules (tacrolimus capsules USP) containing the equivalent of 0.5 mg, 1 mg or 5 mg of anhydrous tacrolimus USP. Inactive ingredients include lactose monohydrate NF, hypromellose USP, croscarmellose sodium NF, and magnesium stearate NF. The 0.5 mg capsule shell contains gelatin NF, titanium dioxide USP and ferric oxide NF, the 1 mg capsule shell contains gelatin NF and titanium dioxide USP, and the 5 mg capsule shell contains gelatin NF, titanium dioxide USP and ferric oxide NF.

Prograf is also available as a sterile solution (tacrolimus injection) containing the equivalent of 5 mg anhydrous tacrolimus USP in 1 mL for administration by intravenous infusion only. Each mL contains polyoxyl 60 hydrogenated castor oil (HCO-60), 200 mg, and dehydrated alcohol, USP, 80.0% v/v. Prograf injection must be diluted with 0.9% Sodium Chloride Injection or 5% Dextrose Injection before use.

Tacrolimus, previously known as FK506, is the active ingredient in Prograf. Tacrolimus is a macrolide immunosuppressant produced by Streptomyces tsukubaensis. Chemically, tacrolimus is designated as [3S-[3R*[E(1S*,3S*,4S*)], 4S*,5R*,8S*,9E,12R*,14R*,15S*,16R*,18S*,19S*,26aR*]] -5,6,8,11,12,13,14,15,16,17,18,19,24,25,26,26a-hexadecahydro-5,19-dihydroxy-3-[2-(4-hydroxy-3-methoxycyclohexyl)-1-methylethenyl]-14,16-dimethoxy-4,10,12,18-tetramethyl-8-(2-propenyl)-15,19-epoxy-3H-pyrido[2,1-c][1,4] oxaazacyclotricosine-1,7,20,21(4H,23H)-tetrone, monohydrate.

The chemical structure of tacrolimus is:

Tacrolimus has an empirical formula of C44H69NO12•H2O and a formula weight of 822.03. Tacrolimus appears as white crystals or crystalline powder. It is practically insoluble in water, freely soluble in ethanol, and very soluble in methanol and chloroform.

12 CLINICAL PHARMACOLOGY

12.1 Mechanism of Action

Tacrolimus inhibits T-lymphocyte activation, although the exact mechanism of action is not known. Experimental evidence suggests that tacrolimus binds to an intracellular protein, FKBP-12. A complex of tacrolimus-FKBP-12, calcium, calmodulin, and calcineurin is then formed and the phosphatase activity of calcineurin inhibited. This effect may prevent the dephosphorylation and translocation of nuclear factor of activated T-cells (NF-AT), a nuclear component thought to initiate gene transcription for the formation of lymphokines (such as interleukin-2, gamma interferon). The net result is the inhibition of T-lymphocyte activation (i.e., immunosuppression).

Tacrolimus prolongs the survival of the host and transplanted graft in animal transplant models of liver, kidney, heart, bone marrow, small bowel and pancreas, lung and trachea, skin, cornea, and limb.

In animals, tacrolimus has been demonstrated to suppress some humoral immunity and, to a greater extent, cell-mediated reactions such as allograft rejection, delayed type hypersensitivity, collagen-induced arthritis, experimental allergic encephalomyelitis, and graft versus host disease.

12.3 Pharmacokinetics

Tacrolimus activity is primarily due to the parent drug. The pharmacokinetic parameters (mean±S.D.) of tacrolimus have been determined following intravenous (IV) and/or oral (PO) administration in healthy volunteers, and in kidney transplant, liver transplant, and heart transplant patients (Table 14).

Table 14. Pharmacokinetics Parameters (mean±S.D.) of Tacrolimus in Healthy Volunteers and Patients
Population | N | Route; (Dose) | Parameters
Population | N | Route; (Dose) | Cmax; (ng/mL) | Tmax; (hr) | AUC; (ng•hr/mL) | t1/2; (hr) | CI; (L/hr/kg) | V; (L/kg)
Healthy; Volunteers | 8 | IV; (0.025 mg/kg/4hr) | [not applicable] |  | 598 [AUC0-120]; ± 125 | 34.2; ± 7.7 | 0.040; ± 0.009 | 1.91; ± 0.31
Healthy; Volunteers | 16 | PO; (5 mg) | 29.7; ± 7.2 | 1.6; ± 0.7 | 243 [AUC0-72]; ± 73 | 34.8; ± 11.4 | 0.041 [Corrected for individual bioavailability]; ± 0.008 | 1.94; ± 0.53
Kidney; Transplant; Patients | 26 | IV; (0.02 mg/kg/12 hr) |  |  | 294 [AUC0-inf]; ± 262 | 18.8; ± 16.7 | 0.083; ± 0.050 | 1.41; ± 0.66
Kidney; Transplant; Patients | 26 | PO; (0.2 mg/kg/day) | 19.2; ± 10.3 | 3.0 | 203; ± 42 | [not available]
Kidney; Transplant; Patients | 26 | PO; (0.3 mg/kg/day) | 24.2; ± 15.8 | 1.5 | 288; ± 93
Liver; Transplant; Patients | 17 | IV; (0.05 mg/kg/12 hr) |  |  | 3300; ± 2130 | 11.7; ± 3.9 | 0.053; ± 0.017 | 0.85; ± 0.30
Liver; Transplant; Patients | 17 | PO; (0.3 mg/kg/day) | 68.5; ± 30.0 | 2.3; ± 1.5 | 519; ± 179
Heart; Transplant Patients | 11 | IV; (0.01 mg/kg/day as a continuous infusion) |  |  | 954 [AUC0-t]; ± 334 | 23.6; ± 9.22 | 0.051; ± 0.015
Heart; Transplant Patients | 11 | PO; (0.075 mg/kg/day) [Determined after the first dose] | 14.7 + 7.79 | 2.1 [0.5-6.0] [Median [range]] | 82.7 [AUC0-12]; ± 63.2
Heart; Transplant Patients | 14 | PO; (0.15 mg/kg/day) | 24.5 ± 13.7 | 1.5 [0.4-4.0] | 142 ± 116

Due to intersubject variability in tacrolimus pharmacokinetics, individualization of dosing regimen is necessary for optimal therapy [see Dosage and Administration (2.6)]. Pharmacokinetic data indicate that whole blood concentrations rather than plasma concentrations serve as the more appropriate sampling compartment to describe tacrolimus pharmacokinetics.
Absorption

Absorption of tacrolimus from the gastrointestinal tract after oral administration is incomplete and variable. The absolute bioavailability of tacrolimus was 17±10% in adult kidney transplant patients (N=26), 22±6% in adult liver transplant patients (N=17), 23±9% in adult heart transplant patients (N=11) and 18±5% in healthy volunteers (N=16).

A single dose trial conducted in 32 healthy volunteers established the bioequivalence of the 1 mg and 5 mg capsules. Another single dose trial in 32 healthy volunteers established the bioequivalence of the 0.5 mg and 1 mg capsules. Tacrolimus maximum blood concentrations (Cmax) and area under the curve (AUC) appeared to increase in a dose-proportional fashion in 18 fasted healthy volunteers receiving a single oral dose of 3, 7, and 10 mg.

In 18 kidney transplant patients, tacrolimus trough concentrations from 3 to 30 ng/mL measured at 10-12 hours post-dose (Cmin) correlated well with the AUC (correlation coefficient 0.93). In 24 liver transplant patients over a concentration range of 10 to 60 ng/mL, the correlation coefficient was 0.94. In 25 heart transplant patients over a concentration range of 2 to 24 ng/mL, the correlation coefficient was 0.89 after an oral dose of 0.075 or 0.15 mg/kg/day at steady-state.
Food Effects

The rate and extent of tacrolimus absorption were greatest under fasted conditions. The presence and composition of food decreased both the rate and extent of tacrolimus absorption when administered to 15 healthy volunteers.

The effect was most pronounced with a high-fat meal (848 kcal, 46% fat): mean AUC and Cmax were decreased 37% and 77%, respectively; Tmax was lengthened 5-fold. A high-carbohydrate meal (668 kcal, 85% carbohydrate) decreased mean AUC and mean Cmax by 28% and 65%, respectively.

In healthy volunteers (N=16), the time of the meal also affected tacrolimus bioavailability. When given immediately following the meal, mean Cmax was reduced 71%, and mean AUC was reduced 39%, relative to the fasted condition. When administered 1.5 hours following the meal, mean Cmax was reduced 63%, and mean AUC was reduced 39%, relative to the fasted condition.

In 11 liver transplant patients, Prograf administered 15 minutes after a high fat (400 kcal, 34% fat) breakfast, resulted in decreased AUC (27±18%) and Cmax (50±19%), as compared to a fasted state.

Prograf capsules should be taken consistently every day either with or without food because the presence and composition of food decreases the bioavailability of Prograf [see Dosage and Administration (2.5)].
Distribution

The plasma protein binding of tacrolimus is approximately 99% and is independent of concentration over a range of 5-50 ng/mL. Tacrolimus is bound mainly to albumin and alpha-1-acid glycoprotein, and has a high level of association with erythrocytes. The distribution of tacrolimus between whole blood and plasma depends on several factors, such as hematocrit, temperature at the time of plasma separation, drug concentration, and plasma protein concentration. In a U.S. trial, the ratio of whole blood concentration to plasma concentration averaged 35 (range 12 to 67).
Metabolism

Tacrolimus is extensively metabolized by the mixed-function oxidase system, primarily the cytochrome P-450 system (CYP3A). A metabolic pathway leading to the formation of 8 possible metabolites has been proposed. Demethylation and hydroxylation were identified as the primary mechanisms of biotransformation in vitro. The major metabolite identified in incubations with human liver microsomes is 13-demethyl tacrolimus. In in vitro studies, a 31-demethyl metabolite has been reported to have the same activity as tacrolimus.
Excretion
The mean clearance following IV administration of tacrolimus is 0.040, 0.083, and 0.053, and 0.051 L/hr/kg in healthy volunteers, adult kidney transplant patients, adult liver transplant patients, and adult heart transplant patients, respectively. In man, less than 1% of the dose administered is excreted unchanged in urine.

In a mass balance study of IV administered radiolabeled tacrolimus to 6 healthy volunteers, the mean recovery of radiolabel was 77.8±12.7%. Fecal elimination accounted for 92.4±1.0% and the elimination half-life based on radioactivity was 48.1±15.9 hours whereas it was 43.5±11.6 hours based on tacrolimus concentrations. The mean clearance of radiolabel was 0.029±0.015 L/hr/kg and clearance of tacrolimus was 0.029±0.009 L/hr/kg. When administered PO, the mean recovery of the radiolabel was 94.9±30.7%. Fecal elimination accounted for 92.6±30.7%, urinary elimination accounted for 2.3±1.1% and the elimination half-life based on radioactivity was 31.9±10.5 hours whereas it was 48.4±12.3 hours based on tacrolimus concentrations. The mean clearance of radiolabel was 0.226±0.116 L/hr/kg and clearance of tacrolimus 0.172±0.088 L/hr/kg.
Specific Populations

Pediatric

Pharmacokinetics of tacrolimus have been studied in liver transplantation patients, 0.7 to 13.2 years of age. Following IV administration of a 0.037 mg/kg/day dose to 12 pediatric patients, mean terminal half-life, volume of distribution and clearance were 11.5±3.8 hours, 2.6±2.1 L/kg and 0.138±0.071 L/hr/kg, respectively. Following oral administration to 9 patients, mean AUC and Cmax were 337±167 ng·hr/mL and 48.4±27.9 ng/mL, respectively. The absolute bioavailability was 31±24%.

Whole blood trough concentrations from 31 patients less than 12 years old showed that pediatric patients needed higher doses than adults to achieve similar tacrolimus trough concentrations [see Dosage and Administration (2.2)].

Pharmacokinetics of tacrolimus have also been studied in kidney transplantation patients, 8.2±2.4 years of age. Following IV infusion of a 0.06 (range 0.06 – 0.09) mg/kg/day to 12 pediatric patients (8 male and 4 female), mean terminal half-life and clearance were 10.2±5.0 (range 3.4-25) hours and 0.12±0.04 (range 0.06-0.17) L/hr/kg, respectively. Following oral administration to the same patients, mean AUC and Cmax were 181±65 (range 81-300) ng·hr/mL and 30±11 (range 14-49) ng/mL, respectively. The absolute bioavailability was 19±14 (range 5.2-56) %.

Renal and Hepatic Impairment
The mean pharmacokinetic parameters for tacrolimus following single administrations to patients with renal and hepatic impairment are given in Table 15.

Table 15. Pharmacokinetic In Renal and Hepatic Impaired Patients
Population; (No. of Patients) | Dose | AUC0-t; (ng·hr/mL) | t1/2; (hr) | V; (L/kg) | CI; (L/hr/kg)
Renal; Impairment; (n=12) | 0.02; mg/kg/4hr; IV | 393±123; (t=60 hr) | 26.3±9.2 | 1.07; ±0.20 | 0.038; ±0.014
Mild Hepatic; Impairment; (n=6) | 0.02; mg/kg/4hr; IV | 367±107; (t=72 hr) | 60.6±43.8; Range: 27.8 – 141 | 3.1±1.6 | 0.042; ±0.02
Mild Hepatic; Impairment; (n=6) | 7.7 mg; PO | 488±320; (t=72 hr) | 66.1±44.8; Range: 29.5 – 138 | 3.7±4.7 [corrected for bioavailability] | 0.034; ±0.019
Severe; Hepatic; Impairment; (n=6, IV) | 0.02 mg/kg/4hr; IV (n=2) 0.01 mg/kg/8hr; IV (n=4) | 762±204; (t=120 hr) 289±117; (t=144 hr) | 198±158; Range: 81-436 | 3.9±1.0 | 0.017; ±0.013
(n=5, PO) [1 patient did not receive the PO dose] | 8 mg PO; (n=1) 5 mg PO; (n=4); 4 mg PO; (n=1) | 658; (t=120 hr) 533±156 (t=144 hr) | 119±35; Range: 85-178 | 3.1±3.4 | 0.016; ±0.011

Renal Impairment: Tacrolimus pharmacokinetics following a single IV administration were determined in 12 patients (7 not on dialysis and 5 on dialysis, serum creatinine of 3.9±1.6 and 12.0±2.4 mg/dL, respectively) prior to their kidney transplant. The pharmacokinetic parameters obtained were similar for both groups. The mean clearance of tacrolimus in patients with renal dysfunction was similar to that in normal volunteers (Table 15) [see Dosage and Administration (2.3) and Use in Specific Populations (8.6)].

Hepatic Impairment: Tacrolimus pharmacokinetics have been determined in six patients with mild hepatic dysfunction (mean Pugh score: 6.2) following single IV and oral administrations. The mean clearance of tacrolimus in patients with mild hepatic dysfunction was not substantially different from that in normal volunteers (see previous table). Tacrolimus pharmacokinetics were studied in 6 patients with severe hepatic dysfunction (mean Pugh score: >10). The mean clearance was substantially lower in patients with severe hepatic dysfunction, irrespective of the route of administration [see Dosage and Administration (2.4) and Use in Specific Populations (8.7)].

Race
The pharmacokinetics of tacrolimus have been studied following single IV and oral administration of Prograf to 10 African-American, 12 Latino-American, and 12 Caucasian healthy volunteers. There were no significant pharmacokinetic differences among the three ethnic groups following a 4-hour IV infusion of 0.015 mg/kg. However, after single oral administration of 5 mg, mean (±SD) tacrolimus Cmax in African-Americans (23.6±12.1 ng/mL) was significantly lower than in Caucasians (40.2±12.6 ng/mL) and the Latino-Americans (36.2±15.8 ng/mL) (p<0.01). Mean AUC0-inf tended to be lower in African-Americans (203±115 ng·hr/mL) than Caucasians (344±186 ng·hr/mL) and Latino-Americans (274±150 ng·hr/mL). The mean (±SD) absolute oral bioavailability (F) in African-Americans (12±4.5%) and Latino-Americans (14±7.4%) was significantly lower than in Caucasians (19±5.8%, p=0.011). There was no significant difference in mean terminal T1/2 among the three ethnic groups (range from approximately 25 to 30 hours). A retrospective comparison of African-American and Caucasian kidney transplant patients indicated that African-American patients required higher tacrolimus doses to attain similar trough concentrations [see Dosage and Administration (2.1)].

Gender
A formal trial to evaluate the effect of gender on tacrolimus pharmacokinetics has not been conducted, however, there was no difference in dosing by gender in the kidney transplant trial. A retrospective comparison of pharmacokinetics in healthy volunteers, and in kidney, liver and heart transplant patients indicated no gender-based differences.
Drug Interactions

Frequent monitoring of whole blood concentrations and appropriate dosage adjustments of tacrolimus are recommended when concomitant use of the following drugs with tacrolimus is initiated or discontinued [see Drug Interactions (7)].

Telaprevir: In a single dose study in 9 healthy volunteers, coadministration of tacrolimus (0.5 mg single dose) with telaprevir (750 mg three times daily for 13 days) increased the tacrolimus dose-normalized Cmax by 9.3-fold and AUC by 70-fold compared to tacrolimus alone [see Drug Interactions (7.3)].

Boceprevir: In a single dose study in 12 subjects, coadministration of tacrolimus (0.5 mg single dose) with boceprevir (800 mg three times daily for 11 days) increased tacrolimus Cmax by 9.9-fold and AUC by 17-fold compared to tacrolimus alone [see Drug Interactions (7.3)].

Nelfinavir: Based on a clinical study of 5 liver transplant recipients, co-administration of tacrolimus with nelfinavir increased blood concentrations of tacrolimus significantly and, as a result, a reduction in the tacrolimus dose by an average of 16-fold was needed to maintain mean trough tacrolimus blood concentrations of 9.7 ng/mL. It is recommended to avoid concomitant use of Prograf and nelfinavir unless the benefits outweigh the risks [see Drug Interactions (7.3)].

Rifampin: In a study of 6 normal volunteers, a significant decrease in tacrolimus oral bioavailability (14±6% vs. 7±3%) was observed with concomitant rifampin administration (600 mg). In addition, there was a significant increase in tacrolimus clearance (0.036±0.008 L/hr/kg vs. 0.053±0.010 L/hr/kg) with concomitant rifampin administration [see Drug Interactions (7.7)].

Magnesium-aluminum-hydroxide: In a single-dose crossover study in healthy volunteers, co-administration of tacrolimus and magnesium-aluminum-hydroxide resulted in a 21% increase in the mean tacrolimus AUC and a 10% decrease in the mean tacrolimus Cmax relative to tacrolimus administration alone [see Drug Interactions (7.10)].

Ketoconazole: In a study of 6 normal volunteers, a significant increase in tacrolimus oral bioavailability (14±5% vs. 30±8%) was observed with concomitant ketoconazole administration (200 mg). The apparent oral clearance of tacrolimus during ketoconazole administration was significantly decreased compared to tacrolimus alone (0.430±0.129 L/hr/kg vs. 0.148±0.043 L/hr/kg). Overall, IV clearance of tacrolimus was not significantly changed by ketoconazole co-administration, although it was highly variable between patients [see Drug Interactions (7.4)].

Voriconazole (see complete prescribing information for VFEND®): Repeat oral dose administration of voriconazole (400 mg every 12 hours for one day, then 200 mg every 12 hours for 6 days) increased tacrolimus (0.1 mg/kg single dose) Cmax and AUCτ in healthy subjects by an average of 2-fold (90% CI: 1.9, 2.5) and 3-fold (90% CI: 2.7, 3.8), respectively [see Drug Interactions (7.4)].

Posaconazole (see complete prescribing information for Noxafil®): Repeat oral administration of posaconazole (400 mg twice daily for 7 days) increased tacrolimus (0.05 mg/kg single dose) Cmax and AUC in healthy subjects by an average of 2-fold (90% CI: 2.01, 2.42) and 4.5-fold (90% CI 4.03, 5.19), respectively [see Drug Interactions (7.4)].

Caspofungin (see complete prescribing information for CANCIDAS®): Caspofungin reduced the blood AUC0-12 of tacrolimus by approximately 20%, peak blood concentration (Cmax) by 16%, and 12-hour blood concentration (C12hr) by 26% in healthy adult subjects when tacrolimus (2 doses of 0.1 mg/kg 12 hours apart) was administered on the 10th day of CANCIDAS® 70 mg daily, as compared to results from a control period in which tacrolimus was administered alone [see Drug Interactions (7.4)].

13 NONCLINICAL TOXICOLOGY

13.1 Carcinogenesis, Mutagenesis, Impairment of Fertility

Carcinogenicity studies were conducted in male and female rats and mice. In the 80-week mouse oral study and in the 104-week rat oral study, no relationship of tumor incidence to tacrolimus dosage was found. The highest dose used in the mouse was 3.0 mg/kg/day (0.9 to 2.2 times the AUC at clinical doses of 0.075 to 0.2 mg/kg/day) and in the rat was 5.0 mg/kg/day (0.265 to 0.65 times the AUC at clinical doses of 0.075 to 0.2 mg/kg/day) [see Boxed Warning and Warnings and Precautions (5.2)].

A 104-week dermal carcinogenicity study was performed in mice with tacrolimus ointment (0.03% - 3%), equivalent to tacrolimus doses of 1.1-118 mg/kg/day or 3.3-354 mg/m^2/day. In the study, the incidence of skin tumors was minimal and the topical application of tacrolimus was not associated with skin tumor formation under ambient room lighting. However, a statistically significant elevation in the incidence of pleomorphic lymphoma in high dose male (25/50) and female animals (27/50) and in the incidence of undifferentiated lymphoma in high dose female animals (13/50) was noted in the mouse dermal carcinogenicity study. Lymphomas were noted in the mouse dermal carcinogenicity study at a daily dose of 3.5 mg/kg (0.1% tacrolimus ointment). No drug-related tumors were noted in the mouse dermal carcinogenicity study at a daily dose of 1.1 mg/kg (0.03% tacrolimus ointment). The relevance of topical administration of tacrolimus in the setting of systemic tacrolimus use is unknown.

The implications of these carcinogenicity studies to the human condition are limited; doses of tacrolimus were administered that likely induced immunosuppression in these animals impairing their immune system’s ability to inhibit unrelated carcinogenesis.

No evidence of genotoxicity was seen in bacterial (Salmonella and E. coli) or mammalian (Chinese hamster lung-derived cells) in vitro assays of mutagenicity, the in vitro CHO/HGPRT assay of mutagenicity, or in vivo clastogenicity assays performed in mice; tacrolimus did not cause unscheduled DNA synthesis in rodent hepatocytes.

Tacrolimus given orally at 1.0 mg/kg (0.8 to 2.2 times the clinical dose range of 0.075 to 0.2 mg/kg/day based on body surface area) to male and female rats, prior to and during mating, as well as to dams during gestation and lactation, was associated with embryolethality and adverse effects on female reproduction. Effects on female reproductive function (parturition) and embryolethal effects were indicated by a higher rate of pre-implantation loss and increased numbers of undelivered and nonviable pups. When given at 3.2 mg/kg (2.6 to 6.9 times the clinical dose range based on body surface area), tacrolimus was associated with maternal and paternal toxicity as well as reproductive toxicity including marked adverse effects on estrus cycles, parturition, pup viability, and pup malformations.

14 CLINICAL STUDIES

14.1 Kidney Transplantation

Prograf/azathioprine (AZA)
Prograf-based immunosuppression in conjunction with azathioprine and corticosteroids following kidney transplantation was assessed in a randomized, multicenter, non-blinded, prospective trial. There were 412 kidney transplant patients enrolled at 19 clinical sites in the United States. Study therapy was initiated when renal function was stable as indicated by a serum creatinine ≤ 4 mg/dL (median of 4 days after transplantation, range 1 to 14 days). Patients less than 6 years of age were excluded.

There were 205 patients randomized to Prograf-based immunosuppression and 207 patients were randomized to cyclosporine-based immunosuppression. All patients received prophylactic induction therapy consisting of an antilymphocyte antibody preparation, corticosteroids and azathioprine. Overall 1 year patient and graft survival was 96.1% and 89.6%, respectively.

Data from this trial of Prograf in conjunction with azathioprine indicate that during the first three months of that trial, 80% of the patients maintained trough concentrations between 7-20 ng/mL, and then between 5-15 ng/mL, through 1 year.

Prograf/mycophenolate mofetil (MMF)
Prograf-based immunosuppression in conjunction with MMF, corticosteroids, and induction has been studied. In a randomized, open-label, multi-center trial (Study 1), 1589 kidney transplant patients received Prograf (Group C, n=401), sirolimus (Group D, n=399), or one of two cyclosporine (CsA) regimens (Group A, n=390 and Group B, n=399) in combination with MMF and corticosteroids; all patients, except those in one of the two cyclosporine groups, also received induction with daclizumab. The trial was conducted outside the United States; the trial population was 93% Caucasian. In this trial, mortality at 12 months in patients receiving Prograf/MMF was similar (3%) compared to patients receiving cyclosporine/MMF (3% and 2%) or sirolimus/MMF (3%). Patients in the Prograf group exhibited higher estimated creatinine clearance rates (eCLcr) using the Cockcroft-Gault formula (Table 16) and experienced fewer efficacy failures, defined as biopsy proven acute rejection (BPAR), graft loss, death, and/or lost to follow-up (Table 17) in comparison to each of the other three groups. Patients randomized to Prograf/MMF were more likely to develop diarrhea and diabetes after the transplantation and experienced similar rates of infections compared to patients randomized to either cyclosporine/MMF regimen [see Adverse Reactions (6.1)].

Table 16. Estimated Creatinine Clearance at 12 Months (Study 1)
Group | eCLcr [mL/min] at Month 12 [All death/graft loss (n=41, 27, 23 and 42 in Groups A, B, C and D) and patients whose last recorded creatinine values were prior to month 3 visit (n=10, 9, 7 and 9 in Groups A, B, C and D, respectively) were inputed with Glomerular Filtration Rate (GFR) of 10 mL/min; a subject's last observed creatinine value from month 3 on was used for the remainder of subjects with missing creatinine at month 12 (n=11, 12, 15 and 19 for Groups A, B, C and D, respectively). Weight was also imputed in the calculation of estimated GFR, if missing.]
Group | N | MEAN | SD | MEDIAN | Treatment Difference with Group C (99.2% CI [Adjusted for multiple (6) pairwise comparisons using Bonferroni corrections.])
(A) CsA/MMF/CS | 390 | 56.5 | 25.8 | 56.9 | -8.6 (-13.7, -3.7)
(B) CsA/MMF/CS/Daclizumab | 399 | 58.9 | 25.6 | 60.9 | -6.2 (-11.2, -1.2)
(C) Tac/MMF/CS/Daclizumab | 401 | 65.1 | 27.4 | 66.2 | -
(D) Siro/MMF/CS/Daclizumab | 399 | 56.2 | 27.4 | 57.3 | -8.9 (-14.1, -3.9)
Total | 1589 | 59.2 | 26.8 | 60.5
Key: CsA=Cyclosporine, CS=Corticosteroids, Tac=Tacrolimus, Siro=Sirolimus

Table 17. Incidence of BPAR, Graft Loss, Death or Loss to Follow-up at 12 Months (Study 1)
 | Group A; N=390 | Group B; N=399 | Group C; N=401 | Group D; N=399
Overall Failure | 141 (36.2%) | 126 (31.6%) | 82 (20.4%) | 185 (46.4%)
Components of efficacy failure
BPAR | 113 (29.0%) | 106 (26.6%) | 60 (15.0%) | 152 (38.1%)
Graft loss excluding death | 28 (7.2%) | 20 (5.0%) | 12 (3.0%) | 30 (7.5%)
Mortality | 13 (3.3%) | 7 (1.8%) | 11 (2.7%) | 12 (3.0%)
Lost to follow-up | 5 (1.3%) | 7 (1.8%) | 5 (1.3%) | 6 (1.5%)
Treatment Difference of efficacy failure compared to Group C (99.2% CI [Adjusted for multiple (6) pairwise comparisons using Bonferroni corrections.]) | 15.8% (7.1%, 24.3%) | 11.2% (2.7%, 19.5%) | - | 26.0% (17.2%, 34.7%)
Key: Group A=CsA/MMF/CS, B=CsA/MMF/CS/Daclizumab, C=Tac/MMF/CS/Daclizumab, and D=Siro/MMF/CS/Daclizumab

The protocol-specified target tacrolimus trough concentrations (Ctrough,Tac) were 3-7 ng/mL; however, the observed median Ctroughs,Tac approximated 7 ng/mL throughout the 12 month trial (Table 18). Approximately 80% of patients maintained tacrolimus whole blood concentrations between 4-11 ng/mL through 1 year post-transplant.

Table 18. Tacrolimus Whole Blood Trough Concentrations (Study 1)
Time | Median (P10-P90 [10 to 90th Percentile: range of Ctrough, Tac that excludes lowest 10% and highest 10% of Ctrough,Tac]) tacrolimus whole blood trough concentrations; (ng/mL)
Day 30 (N=366) | 6.9 (4.4 – 11.3)
Day 90 (N=351) | 6.8 (4.1 – 10.7)
Day 180 (N=355) | 6.5 (4.0 – 9.6)
Day 365 (N=346) | 6.5 (3.8 – 10.0)

The protocol-specified target cyclosporine trough concentrations (Ctrough,CsA) for Group B were 50-100 ng/mL; however, the observed median Ctroughs,CsA approximated 100 ng/mL throughout the 12 month trial. The protocol-specified target Ctroughs,CsA for Group A were 150-300 ng/mL for the first 3 months and 100-200 ng/mL from month 4 to month 12; the observed median Ctroughs, CsA approximated 225 ng/mL for the first 3 months and 140 ng/mL from month 4 to month 12.

While patients in all groups started MMF at 1gram twice daily, the MMF dose was reduced to less than 2 g per day in 63% of patients in the tacrolimus treatment arm by month 12 (Table 19); approximately 50% of these MMF dose reductions were due to adverse reactions. By comparison, the MMF dose was reduced to less than 2 g per day in 49% and 45% of patients in the two cyclosporine arms (Group A and Group B, respectively), by month 12 and approximately 40% of MMF dose reductions were due to adverse reactions.

Table 19. MMF Dose Over Time in Prograf/MMF (Group C) (Study 1)
Time period (Days) | Time-averaged MMF dose (grams per day) [Percentage of patients for each time-averaged MMF dose range during various treatment periods. Administration of 2 g per day of time-averaged MMF dose means that MMF dose was not reduced in those patients during the treatment periods.]
Time period (Days) | Less than 2.0 | 2.0 | Greater than 2.0
0-30 (N=364) | 37% | 60% | 2%
0-90 (N=373) | 47% | 51% | 2%
0-180 (N=377) | 56% | 42% | 2%
0-365 (N=380) | 63% | 36% | 1%
Key: Time-averaged MMF dose = (total MMF dose)/(duration of treatment)

In a second randomized, open-label, multi-center trial (Study 2), 424 kidney transplant patients received Prograf (N=212) or cyclosporine (N=212) in combination with MMF 1 gram twice daily, basiliximab induction, and corticosteroids. In this trial, the rate for the combined endpoint of BPAR, graft failure, death, and/or lost to follow-up at 12 months in the Prograf/MMF group was similar to the rate in the cyclosporine/MMF group. There was, however, an imbalance in mortality at 12 months in those patients receiving Prograf/MMF (4%) compared to those receiving cyclosporine/MMF (2%), including cases attributed to overimmunosuppression (Table 20).

Table 20. Incidence of BPAR, Graft Loss, Death or Loss to Follow-up at 12 Months (Study 2)
 | Prograf/MMF | Cyclosporine/MMF
 | (N=212) | (N=212)
Overall Failure | 32 (15.1%) | 36 (17.0%)
Components of efficacy failure
BPAR | 16 (7.5%) | 29 (13.7%)
Graft loss excluding death | 6 (2.8%) | 4 (1.9%)
Mortality | 9 (4.2%) | 5 (2.4%)
Lost to follow-up | 4 (1.9%) | 1 (0.5%)
Treatment Difference of efficacy failure compared to Prograf/MMF group (95% CI [95% confidence interval calculated using Fisher's Exact Test]) |  | 1.9% (-5.2%, 9.0%)

The protocol-specified target tacrolimus whole blood trough concentrations (Ctrough,Tac) in Study 2 were 7-16 ng/mL for the first three months and 5-15 ng/mL thereafter. The observed median Ctroughs,Tac approximated 10 ng/mL during the first three months and 8 ng/mL from month 4 to month 12 (Table 21). Approximately 80% of patients maintained tacrolimus whole trough blood concentrations between 6 to 16 ng/mL during months 1 through 3 and, then, between 5 to 12 ng/mL from month 4 through 1 year.

Table 21. Tacrolimus Whole Blood Trough Concentrations (Study 2)
Time | Median (P10-P90 [10 to 90th Percentile: range of Ctrough,Tac that excludes lowest 10% and highest 10% of Ctrough, Tac]) tacrolimus whole blood trough concentrations; (ng/mL)
Day 30 (N=174) | 10.5 (6.3 – 16.8)
Day 60 (N=179) | 9.2 (5.9 – 15.3)
Day 120 (N=176) | 8.3 (4.6 – 13.3)
Day 180 (N=171) | 7.8 (5.5 – 13.2)
Day 365 (N=178) | 7.1 (4.2 – 12.4)

The protocol-specified target cyclosporine whole blood concentrations (Ctrough,CsA) were 125 to 400 ng/mL for the first three months, and 100 to 300 ng/mL thereafter. The observed median Ctroughs, CsA approximated 280 ng/mL during the first three months and 190 ng/mL from month 4 to month 12.

Patients in both groups started MMF at 1gram twice daily. The MMF dose was reduced to less than 2 grams per day by month 12 in 62% of patients in the Prograf/MMF group (Table 22) and in 47% of patients in the cyclosporine/MMF group. Approximately 63% and 55% of these MMF dose reductions were because of adverse reactions in the Prograf/MMF group and the cyclosporine/MMF group, respectively [see Adverse Reactions (6.1)].

Table 22. MMF Dose Over Time in the Prograf/MMF Group (Study 2)
Time period (Days) | Time-averaged MMF dose (g/day) [Percentage of patients for each time-averaged MMF dose range during various treatment periods. Two grams per day of time-averaged MMF dose means that MMF dose was not reduced in those patients during the treatment periods.]
Time period (Days) | Less than 2.0 | 2.0 | Greater than 2.0
0-30 (N=212) | 25% | 69% | 6%
0-90 (N=212) | 41% | 53% | 6%
0-180 (N=212) | 52% | 41% | 7%
0-365 (N=212) | 62% | 34% | 4%
Key: Time-averaged MMF dose=(total MMF dose)/(duration of treatment)

14.2 Liver Transplantation

The safety and efficacy of Prograf-based immunosuppression following orthotopic liver transplantation were assessed in two prospective, randomized, non-blinded multicenter trials. The active control groups were treated with a cyclosporine-based immunosuppressive regimen (CsA/AZA). Both trials used concomitant adrenal corticosteroids as part of the immunosuppressive regimens. These trials compared patient and graft survival rates at 12 months following transplantation.

In one trial, 529 patients were enrolled at 12 clinical sites in the United States; prior to surgery, 263 were randomized to the Prograf-based immunosuppressive regimen and 266 to the CsA/AZA. In 10 of the 12 sites, the same CsA/AZA protocol was used, while 2 sites used different control protocols. This trial excluded patients with renal dysfunction, fulminant hepatic failure with Stage IV encephalopathy, and cancers; pediatric patients (≤ 12 years old) were allowed.

In the second trial, 545 patients were enrolled at 8 clinical sites in Europe; prior to surgery, 270 were randomized to the Prograf-based immunosuppressive regimen and 275 to CsA/AZA. In this trial, each center used its local standard CsA/AZA protocol in the active-control arm. This trial excluded pediatric patients, but did allow enrollment of subjects with renal dysfunction, fulminant hepatic failure in Stage IV encephalopathy, and cancers other than primary hepatic with metastases.

One-year patient survival and graft survival in the Prograf-based treatment groups were similar to those in the CsA/AZA treatment groups in both trials. The overall 1-year patient survival (CsA/AZA and Prograf-based treatment groups combined) was 88% in the U.S. trial and 78% in the European trial. The overall 1-year graft survival (CsA/AZA and Prograf-based treatment groups combined) was 81% in the U.S. trial and 73% in the European trial. In both trials, the median time to convert from IV to oral Prograf dosing was 2 days.

Although there is a lack of direct correlation between tacrolimus concentrations and drug efficacy, data from clinical trials of liver transplant patients have shown an increasing incidence of adverse reactions with increasing trough blood concentrations. Most patients are stable when trough whole blood concentrations are maintained between 5 to 20 ng/mL. Long-term post-transplant patients often are maintained at the low end of this target range.

Data from the U.S. clinical trial show that the median trough blood concentrations, measured at intervals from the second week to one year post-transplantation ranged from 9.8 ng/mL to 19.4 ng/mL.

14.3 Heart Transplantation

Two open-label, randomized, comparative trials evaluated the safety and efficacy of Prograf-based and cyclosporine-based immunosuppression in primary orthotopic heart transplantation. In a trial conducted in Europe, 314 patients received a regimen of antibody induction, corticosteroids and azathioprine in combination with Prograf or cyclosporine modified for 18 months. In a 3-arm trial conducted in the US, 331 patients received corticosteroids and Prograf plus sirolimus, Prograf plus mycophenolate mofetil (MMF) or cyclosporine modified plus MMF for 1 year.

In the European trial, patient/graft survival at 18 months post-transplant was similar between treatment arms, 92% in the tacrolimus group and 90% in the cyclosporine group. In the U.S. trial, patient and graft survival at 12 months was similar with 93% survival in the Prograf plus MMF group and 86% survival in the cyclosporine modified plus MMF group. In the European trial, the cyclosporine trough concentrations were above the pre-defined target range (i.e., 100 to 200 ng/mL) at Day 122 and beyond in 32 to 68% of the patients in the cyclosporine treatment arm, whereas the tacrolimus trough concentrations were within the pre-defined target range (i.e., 5 to 15 ng/mL) in 74 to 86% of the patients in the tacrolimus treatment arm. Data from this European trial indicate that from 1 week to 3 months post-transplant, approximately 80% of patients maintained trough concentrations between 8 to 20 ng/mL and, from 3 months through 18 months post-transplant, approximately 80% of patients maintained trough concentrations between 6 to18 ng/mL.

The U.S. trial contained a third arm of a combination regimen of sirolimus, 2 mg per day, and full-dose Prograf; however, this regimen was associated with increased risk of wound healing complications, renal function impairment, and insulin-dependent post-transplant diabetes mellitus, and is not recommended [see Warnings and Precautions (5.12)].

16 HOW SUPPLIED/STORAGE AND HANDLING

Repackaged by Aphena Pharma Solutions - TN.
See Repackaging Information for available configurations.

16.1 Prograf (tacrolimus) Capsules USP

strength | 0.5 mg; (containing the equivalent of 0.5 mg anhydrous tacrolimus USP) | 1 mg; (containing the equivalent of 1 mg anhydrous tacrolimus USP) | 5 mg; (containing the equivalent of 5 mg anhydrous tacrolimus USP)
shape/color | oblong/light yellow | oblong/white | oblong/grayish red
branding on capsule cap/body | 607 | 617 | 657
100 count bottle | NDC 0469-0607-73 | NDC 0469-0617-73 | NDC 0469-0657-73
10 blister cards of 10 capsules | -- | NDC 0469-0617-11 | NDC 0469-0657-11

Made in Ireland

Note: Prograf capsules USP are not filled to maximum capsule capacity. Capsule contains labeled amount.
Store and Dispense

Store at 25°C (77°F); excursions permitted to 15°C-30°C (59°F-86°F).

16.2 Prograf (tacrolimus) Injection

(for IV infusion only)

NDC 0469-3016-01 Product Code 301601

5 mg/mL (equivalent of 5 mg of anhydrous tacrolimus USP per mL) supplied as a sterile solution in a 1 mL ampule, in boxes of 10 ampules

Made in Ireland
Store and Dispense

Store between 5°C and 25°C (41°F and 77°F).

17 PATIENT COUNSELING INFORMATION

17.1 Administration

Advise patients to:

- Take Prograf at the same 12-hour intervals everyday to achieve consistent blood concentrations.
- Take Prograf consistently either with or without food because the presence and composition of food decreases the bioavailability of Prograf.
- Not to eat grapefruit or drink grapefruit juice in combination with Prograf [see Drug Interactions (7.2)].

17.2 Development of Lymphoma and Other Malignancies

Inform patients they are at increased risk of developing lymphomas and other malignancies, particularly of the skin, due to immunosuppression. Advise patients to limit exposure to sunlight and ultraviolet (UV) light by wearing protective clothing and use a sunscreen with a high protection factor [see Warnings and Precautions (5.2)].

17.3 Increased Risk of Infection

Inform patients they are at increased risk of developing a variety of infections, including opportunistic infections, due to immunosuppression and to contact their physician if they develop any symptoms of infection [see Warnings and Precautions (5.3, 5.4, 5.5)].

17.4 New Onset Diabetes After Transplant

Inform patients that Prograf can cause diabetes mellitus and should be advised to contact their physician if they develop frequent urination, increased thirst or hunger [see Warnings and Precautions (5.6)].

17.5 Nephrotoxicity

Inform patients that Prograf can have toxic effects on the kidney that should be monitored. Advise patients to attend all visits and complete all blood tests ordered by their medical team [see Warnings and Precautions (5.7)].

17.6 Neurotoxicity

Inform patients that they are at risk of developing adverse neurologic effects including seizure, altered mental status, and tremor. Advise patients to contact their physician should they develop vision changes, deliriums, or tremors [see Warnings and Precautions (5.8)].

17.7 Hyperkalemia

Inform patients that Prograf can cause hyperkalemia. Monitoring of potassium levels may be necessary, especially with concomitant use of other drugs known to cause hyperkalemia [see Warnings and Precautions (5.9)].

17.8 Hypertension

Inform patients that Prograf can cause high blood pressure which may require treatment with anti-hypertensive therapy [see Warnings and Precautions (5.10)].

17.9 Drug Interactions

Instruct patients to tell their health care providers when they start or stop taking all the medicines, including prescription medicines and non-prescription medicines, natural or herbal remedies, nutritional supplements and vitamins [see Drug Interactions (7)].

17.10 Pregnant Women and Nursing Mothers

Instruct patients to tell their healthcare provider if they plan to become pregnant or breast-feed their infant [see Use in Specific Populations (8.1, 8.3)]

17.11 Immunizations

Inform patients that Prograf can interfere with the usual response to immunizations and that they should avoid live vaccines [see Warnings and Precautions (5.16)].

Rx only

Product of Japan

Manufactured by:
Astellas Ireland Co., Ltd.
Killorglin, County Kerry, Ireland

Marketed by:
Astellas Pharma US, Inc.
Northbrook, IL 60062

Revised: September 2013

13H057-PRG

PATIENT INFORMATION

PROGRAF[PRO-graf]

(tacrolimus) capsules USP

Read this Patient Information before you start taking PROGRAF and each time you get a refill. There may be new information. This information does not take the place of talking with your doctor about your medical condition or your treatment.
What is the most important information I should know about PROGRAF?

Prograf can cause serious side effects, including:

1. Increased risk of cancer. People who take Prograf have an increased risk of getting some kinds of cancer, including skin and lymph gland cancer (lymphoma).
2. Increased risk of infection. PROGRAF is a medicine that affects your immune system. Prograf can lower the ability of your immune system to fight infections. Serious infections can happen in people receiving Prograf that can cause death. Call your doctor right away if you have symptoms of an infection such as:
  - fever
  - sweats or chills
  - cough or flu-like symptoms
  - muscle aches
  - warm, red, or painful areas on your skin

What is PROGRAF?

PROGRAF is a prescription medicine used with other medicines to help prevent organ rejection in people who have had a kidney, liver, or heart transplant and PROGRAF is not for use with medicines called cyclosporines (Gengraf®, Neoral®, and Sandimune®).

PROGRAF is not for use with a medicine called sirolimus (Rapamune®) in people who have had a liver or heart transplants.

It is not known if PROGRAF is safe and effective when used with sirolimus in people who have had kidney transplants.

It is not known if PROGRAF is safe and effective in children who have had a kidney or heart transplants.
Who Should Not Take PROGRAF?

Do not take PROGRAF if you are allergic to tacrolimus or any of the ingredients in PROGRAF. See the end of this leaflet for a complete list of ingredients in PROGRAF.
What should I tell my doctor before taking PROGRAF?

Before you take PROGRAF, tell your doctor if you:

- plan to receive any live vaccines
- have or have had liver, kidney or heart problems
- are pregnant or plan to become pregnant. PROGRAF may harm your unborn baby. Talk to your doctor if you are pregnant or plan to become pregnant.
- Are breastfeeding or plan to breastfeed. PROGRAF can pass into your breast milk. You and your doctor should decide if you will take PROGRAF or breastfeed. You should not do both.

Tell your doctor about all the medicines you take, including prescription and non-prescription medicines, vitamins, and herbal supplements.

Especially tell your doctor if you take:

- cyclosporine (Gengraf®, Neoral®, and Sandimune®)
- sirolimus (Rapamune®)
- nelfinavir (Viracept®)
- telaprevir (IncivekTM)
- boceprevir (VictrelisTM)
- amiodarone (CordaroneTM, NexteroneTM, PaceroneTM)

Ask your doctor or pharmacist if you are not sure if you take any of the medicines listed above.

PROGRAF may affect the way other medicines work, and other medicines may affect how PROGRAF works.

Know the medicines you take. Keep a list of your medicines and show it to your doctor and pharmacist when you get a new medicine.
How Should I Take PROGRAF?

- Take PROGRAF exactly as your doctor tells you to take it.
- Your doctor will tell you how many PROGRAF to take and when to take them.
- Your doctor may change your PROGRAF dose if needed. Do not stop taking or change your dose of PROGRAF without talking to your doctor.
- Take PROGRAF with or without food.
- Take PROGRAF the same way everyday. For example, if you choose to take PROGRAF with food, you should always take PROGRAF with food.
- Take PROGRAF at the same time each day, 12 hours apart. For example, if you take your first dose at 7:00 a.m. you should take your second dose at 7:00 p.m.
  ∘ Taking PROGRAF at the same time each day helps to keep enough medicine in your body to give your transplanted organ the around-the-clock medicine it needs.
- Do not eat grapefruit or drink grapefruit juice while taking PROGRAF.
- If you take too much PROGRAF, call your doctor or go to the nearest hospital emergency room right away.

What should I avoid while taking PROGRAF?

- While you take PROGRAF you should not receive any live vaccines such as:
  ° flu vaccine through your nose
  ° measles
  ° mumps
  ° rubella
  ° polio by mouth
  ° BCG (TB vaccine)
  ° yellow fever
  ° chicken pox (varicella)
  ° typhoid
- Avoid exposure to sunlight and UV light such as tanning machines. Wear protective clothing and use a sunscreen.

What are the possible side effects of PROGRAF?

PROGRAF may cause serious side effects, including:

- See “What the most important information I should know about PROGRAF?”
- high blood sugar (diabetes). Your doctor may do certain tests to check for diabetes while you take PROGRAF. Call your doctor right away if you have:
  ∘ frequent urination
  ∘ increased thirst or hunger
  ∘ blurred vision
  ∘ confusion
  ∘ drowsiness
  ∘ loss of appetite
  ∘ fruity smell on your breath
  ∘ nausea, vomiting, or stomach pain
- kidney problems. Your doctor may do certain tests to check your kidney function while you take PROGRAF.
- nervous system problems. Call your doctor right away if you get any of these symptoms while taking PROGRAF. These could be signs of a serious nervous system problem:
  ∘ confusion
  ∘ coma
  ∘ muscle tremors
  ∘ numbness and tingling
  ∘ headache
  ∘ seizures
  ∘ vision changes
- high levels of potassium in your blood. Your doctor may do certain tests to check your potassium level while you take PROGRAF.
- high blood pressure. Your doctor will monitor your blood pressure while you take PROGRAF.
- heart problems (myocardial hypertrophy). Tell your doctor right away if you get any of these symptoms of heart problems while taking PROGRAF:
  ∘ shortness of breath
  ∘ chest pain
  ∘ feel lightheaded
  ∘ feel faint

The most common side effects of PROGRAF in people receiving kidney transplant are:

- infection
- tremors (shaking of the body)
- high blood pressure
- kidney problems
- constipation
- diarrhea
- headache
- stomach pain
- trouble sleeping
- nausea
- low levels of phosphate in your blood
- swelling of the hands, ankles, or legs
- weakness
- pain
- high levels of fat in your blood
- high levels of potassium in your blood
- low red blood cell count (anemia)

The most common side effects of PROGRAF in people receiving liver transplants are:

- shaking of the body tremors
- headache
- diarrhea
- high blood pressure
- nausea
- kidney problems
- stomach pain
- trouble sleeping
- numbness or tingling in your hands or feet
- anemia
- pain
- fever
- weakness
- high levels of potassium in the blood
- low levels of magnesium in the blood

The most common side effects of PROGRAF for heart transplant patients are:

- kidney problems
- high blood pressure

Tell your doctor if you have any side effect that bothers you or that does not go away.

These are not all the possible side effects of PROGRAF. For more information, ask your doctor or pharmacist.

Call your doctor for medical advice about side effects. You may report side effects to FDA at 1-800-FDA-1088.
How should I store PROGRAF?

- Store PROGRAF at 59º F to 86ºF (15°C to 30º C).
- Safely throw away medicine that is out of date or no longer needed.

Keep PROGRAF and all medicines out of reach of children.
General information about the safe and effective use of PROGRAF

Medicines are sometimes prescribed for purposes other than those listed in a Patient Information leaflet. Do not use PROGRAF for a condition for which it was not prescribed. Do not give PROGRAF to other people, even if they have the same symptoms that you have. It may harm them.
How Does PROGRAF Protect My New Organ?

The body’s immune system protects the body against anything that it does not recognize as part of the body. For example, when the immune system detects a virus or bacteria it tries to get rid of it to prevent infection. When a person has a liver, kidney, or heart transplant, the immune system does not recognize the new organ as a part of the body and tries to get rid of it, too. This is called “rejection”. PROGRAF protects your new organ by slowing down the body’s immune system.

This Patient Information leaflet summarizes the most important information about PROGRAF. If you would like more information, talk with your doctor. You can ask your pharmacist or doctor for information about PROGRAF that is written for health professionals.

For more information, go to www.astellas.com/us or call 1-800-727-7003.
What are the ingredients in PROGRAF?

Active ingredient: tacrolimus

Inactive ingredients: lactose monohydrate, hypromellose, croscarmellose sodium, magnesium stearate, gelatin, titanium dioxide and ferric oxide.
This Patient Information has been approved by the U.S. Food and Drug Administration.
Product of Japan

Manufactured by:
Astellas Ireland Co., Ltd.
Killorglin, County Kerry, Ireland

Marketed by:
Astellas Pharma US, Inc.
Northbrook, IL 60062

Revised: September 2013

13H057-PRG-PI

Repackaging Information

Please reference the How Supplied section listed above for a description of individual tablets or capsules. This drug product has been received by Aphena Pharma - TN in a manufacturer or distributor packaged configuration and repackaged in full compliance with all applicable cGMP regulations. The package configurations available from Aphena are listed below:

Count | 1mg
60 | 43353-178-53
90 | 43353-178-60
180 | 43353-178-80
9000 | 43353-178-09

Store between 20°-25°C (68°-77°F). See USP Controlled Room Temperature. Dispense in a tight light-resistant container as defined by USP. Keep this and all drugs out of the reach of children.

Repackaged by:
Cookeville, TN 38506
20140520SC

PRINCIPAL DISPLAY PANEL - 1mg

NDC 43353-178 - Tacrolimus (Prograf®) 1mg - Rx Only